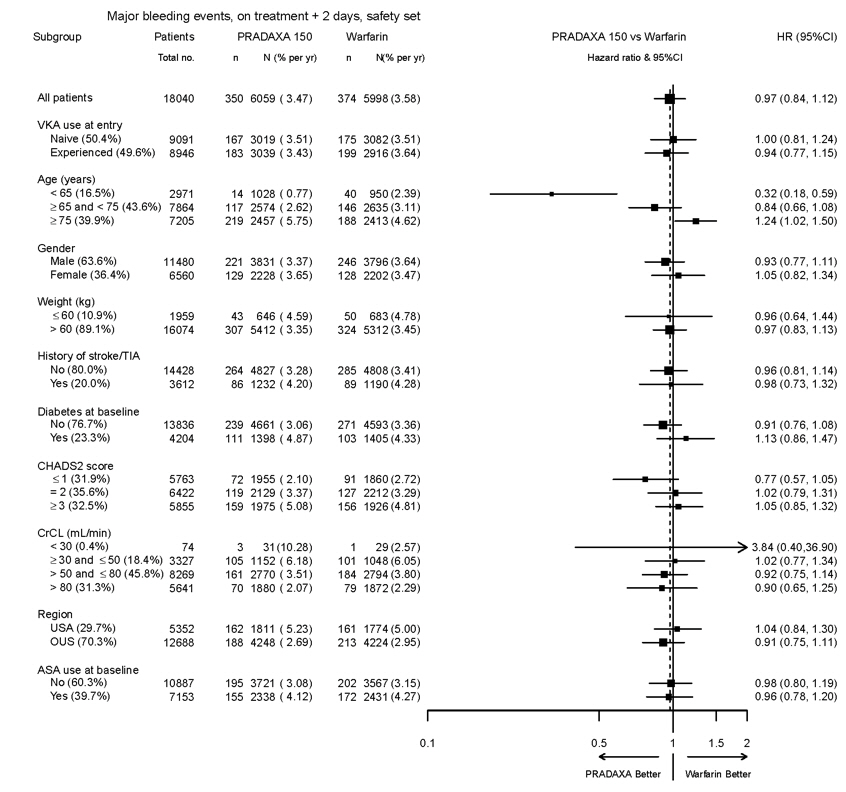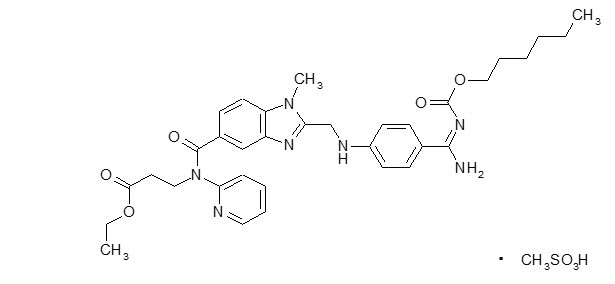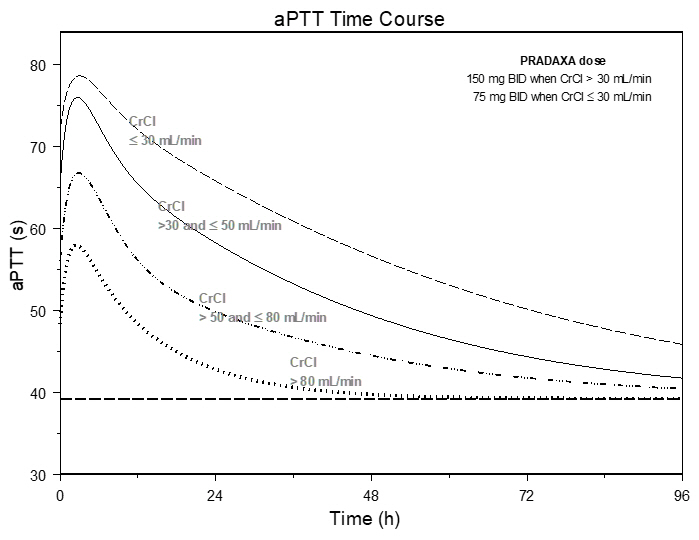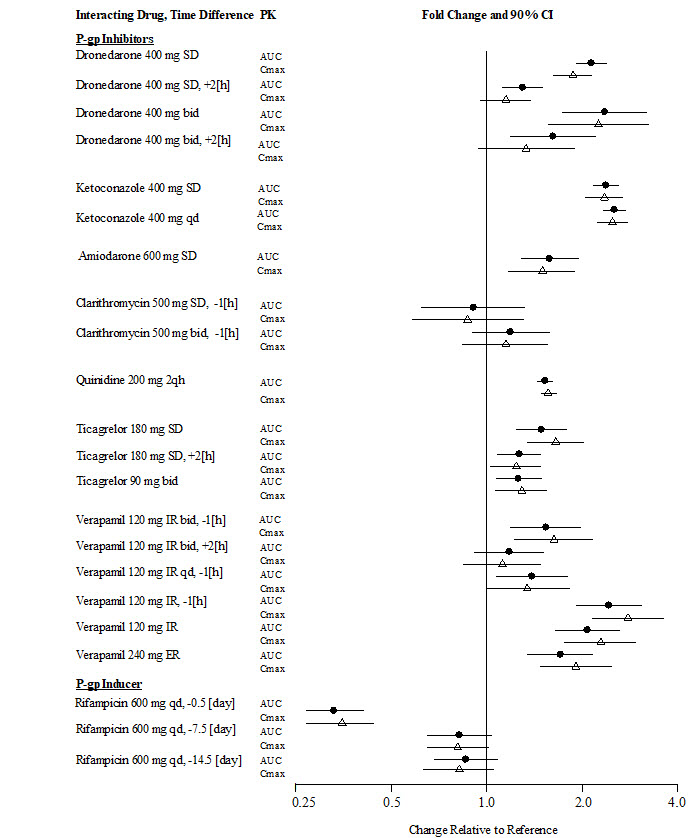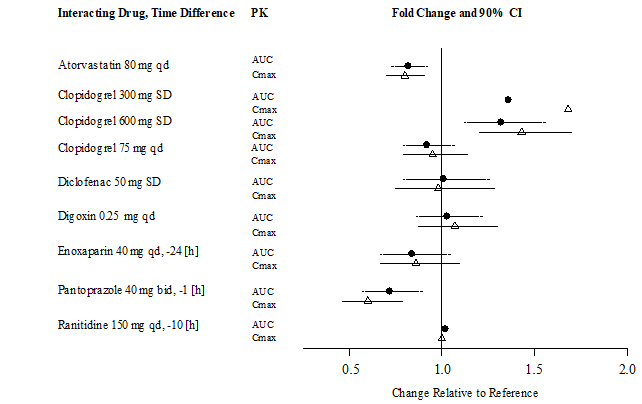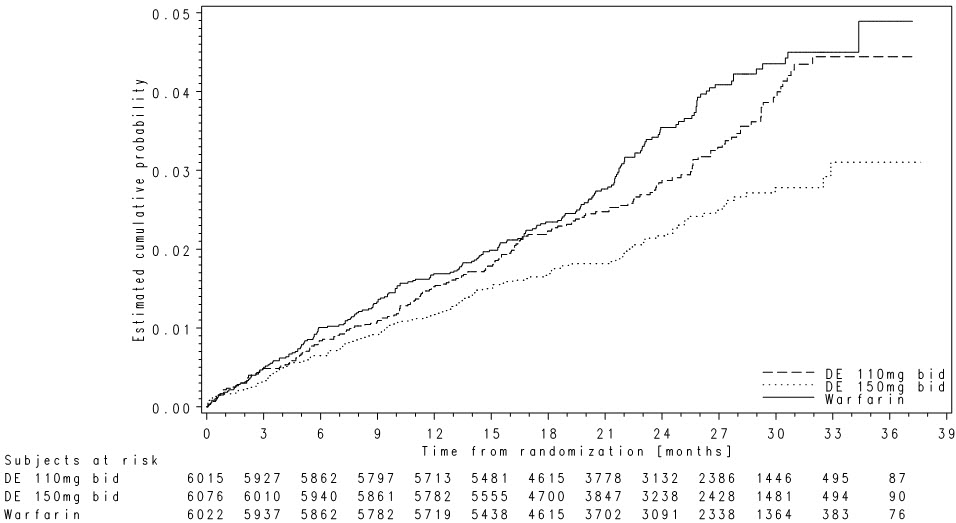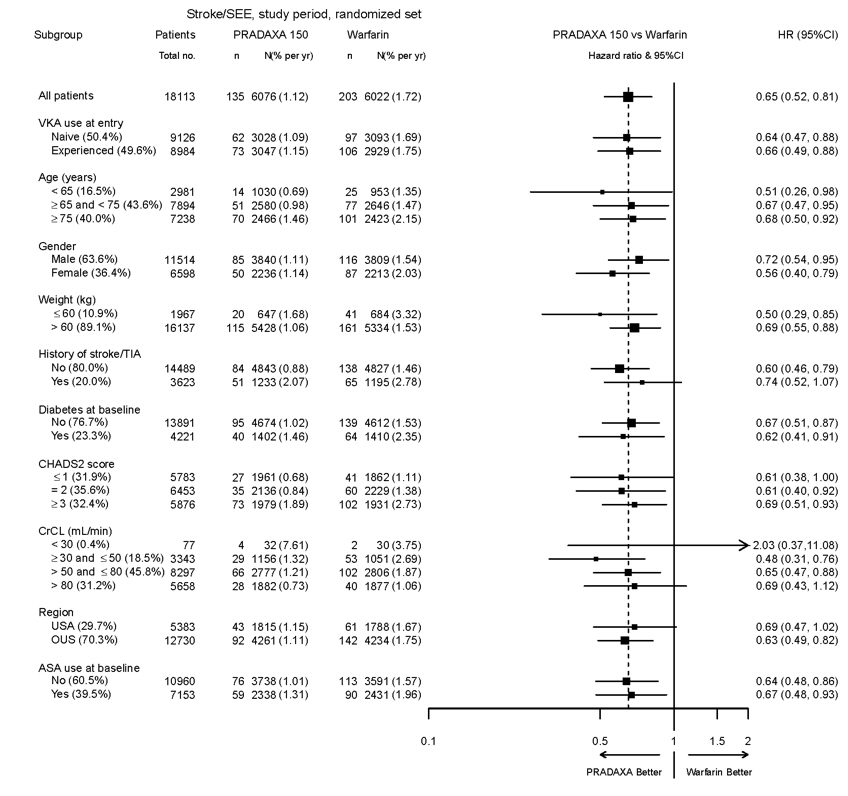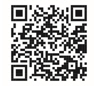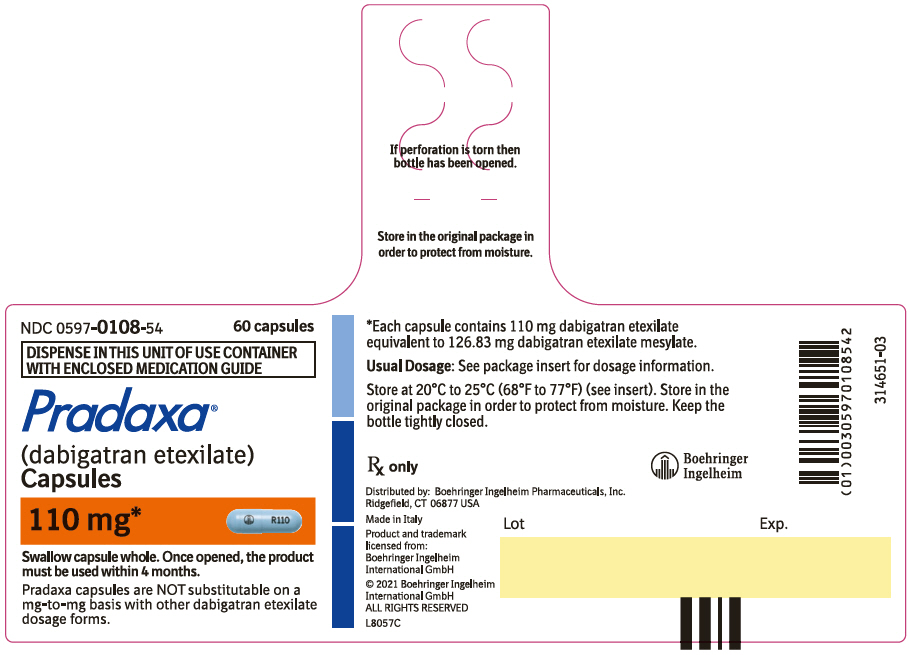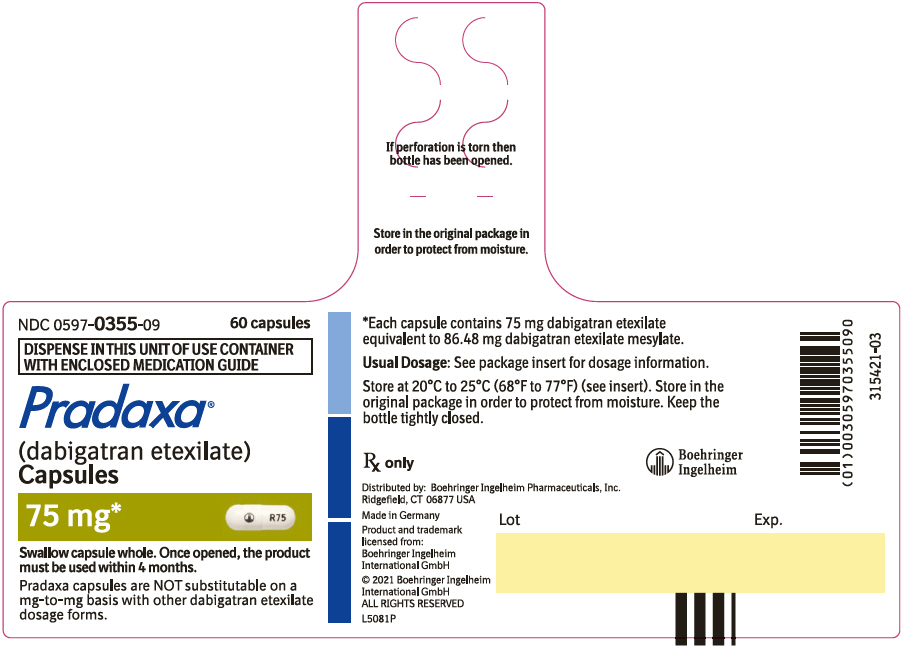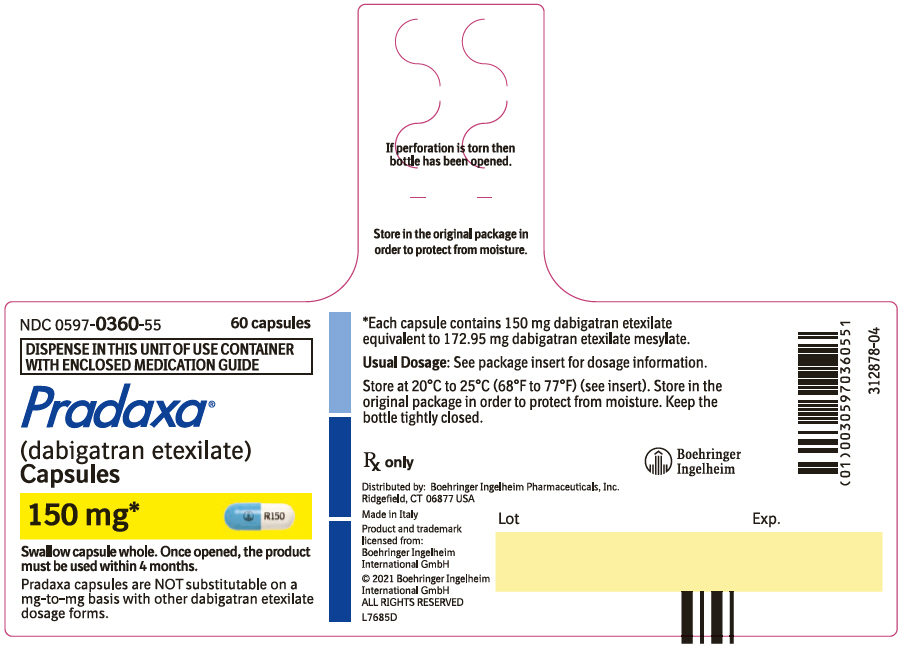 DRUG LABEL: Pradaxa
NDC: 0597-0108 | Form: CAPSULE
Manufacturer: Boehringer Ingelheim Pharmaceuticals Inc.
Category: prescription | Type: HUMAN PRESCRIPTION DRUG LABEL
Date: 20250625

ACTIVE INGREDIENTS: DABIGATRAN ETEXILATE MESYLATE 110 mg/1 1

HIGHLIGHTS OF PRESCRIBING INFORMATION

These highlights do not include all the information needed to use PRADAXA Capsules safely and effectively. See full prescribing information for PRADAXA Capsules.
PRADAXA® (dabigatran etexilate) capsules, for oral use
Initial U.S. Approval: 2010

WARNING: (A) PREMATURE DISCONTINUATION OF PRADAXA INCREASES THE RISK OF THROMBOTIC EVENTS, and (B) SPINAL/EPIDURAL HEMATOMA

See full prescribing information for complete boxed warning

(A) PREMATURE DISCONTINUATION OF PRADAXA INCREASES THE RISK OF THROMBOTIC EVENTS: Premature discontinuation of any oral anticoagulant, including PRADAXA, increases the risk of thrombotic events. To reduce this risk, consider coverage with another anticoagulant if PRADAXA is discontinued for a reason other than pathological bleeding or completion of a course of therapy (2.6, 2.7, 2.8, 5.1).

(B) SPINAL/EPIDURAL HEMATOMA: Epidural or spinal hematomas may occur in patients treated with PRADAXA who are receiving neuraxial anesthesia or undergoing spinal puncture. These hematomas may result in long-term or permanent paralysis (5.3). Monitor patients frequently for signs and symptoms of neurological impairment and if observed, treat urgently. Consider the benefits and risks before neuraxial intervention in patients who are or who need to be anticoagulated (5.3).

1 INDICATIONS AND USAGE

PRADAXA Capsules is a direct thrombin inhibitor indicated:

- To reduce the risk of stroke and systemic embolism in adult patients with non-valvular atrial fibrillation (1.1)
- For the treatment of deep venous thrombosis (DVT) and pulmonary embolism (PE) in adult patients who have been treated with a parenteral anticoagulant for 5-10 days (1.2)
- To reduce the risk of recurrence of DVT and PE in adult patients who have been previously treated (1.3)
- For the prophylaxis of DVT and PE in adult patients who have undergone hip replacement surgery (1.4)
- For the treatment of venous thromboembolic events (VTE) in pediatric patients 8 to less than 18 years of age who have been treated with a parenteral anticoagulant for at least 5 days (1.5)
- To reduce the risk of recurrence of VTE in pediatric patients 8 to less than 18 years of age who have been previously treated (1.6)

2 DOSAGE AND ADMINISTRATION

- Non-valvular Atrial Fibrillation in Adult Patients:
  - For patients with CrCl > 30 mL/min: 150 mg orally, twice daily (2.2)
  - For patients with CrCl 15-30 mL/min: 75 mg orally, twice daily (2.2)
- Treatment of DVT and PE in Adult Patients:
  - For patients with CrCl > 30 mL/min: 150 mg orally, twice daily after 5-10 days of parenteral anticoagulation (2.2)
- Reduction in the Risk of Recurrence of DVT and PE in Adult Patients:
  - For patients with CrCl > 30 mL/min: 150 mg orally, twice daily after previous treatment (2.2)
- Prophylaxis of DVT and PE Following Hip Replacement Surgery in Adult Patients:
  - For patients with CrCl > 30 mL/min: 110 mg orally first day, then 220 mg once daily (2.2)
- Treatment of Pediatric VTE:
  - For pediatric patients: weight-based dosage, twice daily after at least 5 days of parenteral anticoagulant (2.3)
- Reduction in the Risk of Recurrence of Pediatric VTE:
  - For pediatric patients: weight-based dosage, twice daily after previous treatment (2.3)
- Pradaxa Capsules are NOT substitutable on a milligram-to-milligram basis with other dabigatran etexilate dosage forms
- Review recommendations for converting to or from other oral or parenteral anticoagulants (2.6, 2.7)
- Temporarily discontinue PRADAXA before invasive or surgical procedures when possible, then restart promptly (2.8)

3 DOSAGE FORMS AND STRENGTHS

Capsules: 75 mg, 110 mg and 150 mg (3)

4 CONTRAINDICATIONS

- Active pathological bleeding (4)
- History of serious hypersensitivity reaction to PRADAXA (4)
- Mechanical prosthetic heart valve (4)

5 WARNINGS AND PRECAUTIONS

- Bleeding: PRADAXA can cause serious and fatal bleeding (5.2)
- Bioprosthetic heart valves: PRADAXA use not recommended (5.4)
- Increased Risk of Thrombosis in Patients with Triple-Positive Antiphospholipid Syndrome: PRADAXA use not recommended (5.6)

6 ADVERSE REACTIONS

Most common adverse reactions (> 15%) are gastrointestinal adverse reactions and bleeding (6.1)

To report SUSPECTED ADVERSE REACTIONS, contact Boehringer Ingelheim Pharmaceuticals, Inc. at (800) 542-6257 or FDA at 1-800-FDA-1088 or www.fda.gov/medwatch.

7 DRUG INTERACTIONS

- P-gp inducers: Avoid coadministration with PRADAXA (5.5)
- P-gp inhibitors in adult patients with CrCl 30-50 mL/min: Reduce dosage or avoid (7)
- P-gp inhibitors in adult patients with CrCl < 30 mL/min: Not recommended (7)

8 USE IN SPECIFIC POPULATIONS

- Lactation: Breastfeeding not recommended (8.2)
- Geriatric Use: Risk of bleeding increases with age (8.5)

FULL PRESCRIBING INFORMATION

WARNING: (A) PREMATURE DISCONTINUATION OF PRADAXA INCREASES THE RISK OF THROMBOTIC EVENTS, and (B) SPINAL/EPIDURAL HEMATOMA

(A) PREMATURE DISCONTINUATION OF PRADAXA INCREASES THE RISK OF THROMBOTIC EVENTS

Premature discontinuation of any oral anticoagulant, including PRADAXA, increases the risk of thrombotic events. If anticoagulation with PRADAXA is discontinued for a reason other than pathological bleeding or completion of a course of therapy, consider coverage with another anticoagulant [see Dosage and Administration (2.6, 2.7, 2.8) and Warnings and Precautions (5.1)].

(B) SPINAL/EPIDURAL HEMATOMA

Epidural or spinal hematomas may occur in patients treated with PRADAXA who are receiving neuraxial anesthesia or undergoing spinal puncture. These hematomas may result in long-term or permanent paralysis. Consider these risks when scheduling patients for spinal procedures. Factors that can increase the risk of developing epidural or spinal hematomas in these patients include:

- use of indwelling epidural catheters
- concomitant use of other drugs that affect hemostasis, such as non-steroidal anti-inflammatory drugs (NSAIDs), platelet inhibitors, other anticoagulants
- a history of traumatic or repeated epidural or spinal punctures
- a history of spinal deformity or spinal surgery
- optimal timing between the administration of PRADAXA and neuraxial procedures is not known

[see Warnings and Precautions (5.3)].

Monitor patients frequently for signs and symptoms of neurological impairment. If neurological compromise is noted, urgent treatment is necessary [see Warnings and Precautions (5.3)].

Consider the benefits and risks before neuraxial intervention in patients anticoagulated or to be anticoagulated [see Warnings and Precautions (5.3)].

1 INDICATIONS AND USAGE

1.1 Reduction of Risk of Stroke and Systemic Embolism in Non-valvular Atrial Fibrillation in Adult Patients

PRADAXA Capsules is indicated to reduce the risk of stroke and systemic embolism in adult patients with non-valvular atrial fibrillation.

1.2 Treatment of Deep Venous Thrombosis and Pulmonary Embolism in Adult Patients

PRADAXA Capsules is indicated for the treatment of deep venous thrombosis and pulmonary embolism in adult patients who have been treated with a parenteral anticoagulant for 5-10 days.

1.3 Reduction in the Risk of Recurrence of Deep Venous Thrombosis and Pulmonary Embolism in Adult Patients

PRADAXA Capsules is indicated to reduce the risk of recurrence of deep venous thrombosis and pulmonary embolism in adult patients who have been previously treated.

1.4 Prophylaxis of Deep Vein Thrombosis and Pulmonary Embolism in Adult Patients Following Hip Replacement Surgery

PRADAXA Capsules is indicated for the prophylaxis of deep vein thrombosis and pulmonary embolism in adult patients who have undergone hip replacement surgery.

1.5 Treatment of Venous Thromboembolic Events in Pediatric Patients

PRADAXA Capsules is indicated for the treatment of venous thromboembolic events (VTE) in pediatric patients 8 to less than 18 years of age who have been treated with a parenteral anticoagulant for at least 5 days [see Dosage and Administration (2.3)].

1.6 Reduction in the Risk of Recurrence of Venous Thromboembolic Events in Pediatric Patients

PRADAXA Capsules is indicated to reduce the risk of recurrence of VTE in pediatric patients 8 to less than 18 years of age who have been previously treated [see Dosage and Administration (2.3)].

2 DOSAGE AND ADMINISTRATION

2.1 Important Dosage Information

Dabigatran etexilate is available in different dosage forms and not all dosage forms are approved for the same indications and age groups. In addition, there are differences between the dosage forms with respect to dosing due to differences in bioavailability. Do not substitute different dosage forms on a milligram-to-milligram basis and do not combine more than one dosage form to achieve the total dose [see Clinical Pharmacology (12.3)].

2.2 Recommended PRADAXA Capsules Dosage for Adults

Indication | Dosage
Reduction in Risk of Stroke and Systemic Embolism in Non-valvular AF | CrCl > 30 mL/min: | 150 mg twice daily
Reduction in Risk of Stroke and Systemic Embolism in Non-valvular AF | CrCl 15 to 30 mL/min: | 75 mg twice daily
Reduction in Risk of Stroke and Systemic Embolism in Non-valvular AF | CrCl < 15 mL/min or on dialysis: | Dosing recommendations cannot be provided
 | CrCl 30 to 50 mL/min with concomitant use of P-gp inhibitors: | Reduce dosage to 75 mg twice daily if given with P-gp inhibitors dronedarone or systemic ketoconazole.
 | CrCl < 30 mL/min with concomitant use of P-gp inhibitors: | Avoid coadministration
Treatment of DVT and PE | CrCl > 30 mL/min: | 150 mg twice daily
Reduction in the Risk of Recurrence of DVT and PE | CrCl ≤ 30 mL/min or on dialysis: | Dosing recommendations cannot be provided
 | CrCl < 50 mL/min with concomitant use of P-gp inhibitors: | Avoid coadministration
Prophylaxis of DVT and PE Following Hip Replacement Surgery | CrCl > 30 mL/min: | 110 mg for first day, then 220 mg once daily
 | CrCl ≤ 30 mL/min or on dialysis: | Dosing recommendations cannot be provided
 | CrCl < 50 mL/min with concomitant use of P-gp inhibitors: | Avoid coadministration

Reduction of Risk of Stroke and Systemic Embolism in Non-valvular Atrial Fibrillation in Adult Patients

For patients with creatinine clearance (CrCl) > 30 mL/min, the recommended dosage of PRADAXA Capsules is 150 mg taken orally, twice daily. For patients with severe renal impairment (CrCl 15-30 mL/min), the recommended dosage of PRADAXA Capsules is 75 mg twice daily [see Use in Specific Populations (8.6) and Clinical Pharmacology (12.3)]. Dosing recommendations for patients with a CrCl < 15 mL/min or on dialysis cannot be provided.

Treatment of Deep Venous Thrombosis and Pulmonary Embolism in Adult Patients

For patients with CrCl > 30 mL/min, the recommended dosage of PRADAXA Capsules is 150 mg taken orally, twice daily, after 5-10 days of parenteral anticoagulation. Dosing recommendations for patients with a CrCl ≤ 30 mL/min or on dialysis cannot be provided [see Use in Specific Populations (8.6) and Clinical Pharmacology (12.3)].

Reduction in the Risk of Recurrence of Deep Venous Thrombosis and Pulmonary Embolism in Adult Patients

For patients with CrCl > 30 mL/min, the recommended dosage of PRADAXA Capsules is 150 mg taken orally, twice daily after previous treatment. Dosing recommendations for patients with a CrCl ≤ 30 mL/min or on dialysis cannot be provided [see Use in Specific Populations (8.6) and Clinical Pharmacology (12.3)].

Prophylaxis of Deep Vein Thrombosis and Pulmonary Embolism in Adult Patients Following Hip Replacement Surgery

For patients with CrCl > 30 mL/min, the recommended dosage of PRADAXA Capsules is 110 mg taken orally 1-4 hours after surgery and after hemostasis has been achieved, then 220 mg taken once daily for 28-35 days. If PRADAXA is not started on the day of surgery, after hemostasis has been achieved initiate treatment with 220 mg once daily. Dosing recommendations for patients with a CrCl ≤ 30 mL/min or on dialysis cannot be provided [see Dosage and Administration (2.4), Use in Specific Populations (8.6), and Clinical Pharmacology (12.2, 12.3)].

2.3 Recommended PRADAXA Capsules Dosage for Pediatrics

PRADAXA Capsules can be used in pediatric patients aged 8 to less than 18 years of age who are able to swallow the capsules whole. Other age-appropriate pediatric dosage forms of dabigatran etexilate are available for pediatric patients less than 8 years of age. For the treatment of VTE in pediatric patients, initiate treatment following treatment with a parenteral anticoagulant for at least 5 days. For reduction in risk of recurrence of VTE, initiate treatment following previous treatment.

PRADAXA Capsules is dosed orally twice daily, one dose in the morning and one dose in the evening, at approximately the same time every day. The dosing interval should be as close to 12 hours as possible.

The recommended dosage of PRADAXA Capsules for the treatment of or reducing the risk of VTE in pediatric patients 8 to less than 18 years of age is based on the patient's actual weight as shown in Table 1 below. Administer PRADAXA twice daily. Adjust the dosage according to actual weight as treatment progresses [see Dosage and Administration (2.5)].

Table 1 Weight-Based PRADAXA Capsules Dosage for Pediatric Patients Aged 8 to Less Than 18 Years
Actual Weight (kg) | Dosage (mg) | Number of Capsules Needed
11 kg to less than 16 kg | 75 mg twice daily | one 75 mg capsule twice daily
16 kg to less than 26 kg | 110 mg twice daily | one 110 mg capsule twice daily
26 kg to less than 41 kg | 150 mg twice daily | one 150 mg capsule twice daily or two 75 mg capsules twice daily
41 kg to less than 61 kg | 185 mg twice daily | one 110 mg capsule plus one 75 mg capsule twice daily
61 kg to less than 81 kg | 220 mg twice daily | two 110 mg capsule twice daily
81 kg or greater | 260 mg twice daily | one 150 mg capsule plus one 110 mg capsule twice daily or one 110 mg capsule plus two 75 mg capsules twice daily

2.4 Dosage Adjustments

Adult patients with renal impairment

Assess renal function prior to initiation of treatment with PRADAXA Capsules. Periodically assess renal function as clinically indicated (i.e., more frequently in clinical situations that may be associated with a decline in renal function) and adjust therapy accordingly. Discontinue PRADAXA in patients who develop acute renal failure while on PRADAXA and consider alternative anticoagulant therapy.

Generally, in adult patients, the extent of anticoagulation does not need to be assessed. When necessary, use aPTT or ECT, and not INR, to assess for anticoagulant activity in adult patients on PRADAXA Capsules [see Warnings and Precautions (5.2) and Clinical Pharmacology (12.2)].

Reduction of Risk of Stroke and Systemic Embolism in Non-valvular Atrial Fibrillation

In patients with moderate renal impairment (CrCl 30-50 mL/min), concomitant use of the P-gp inhibitor dronedarone or systemic ketoconazole can be expected to produce dabigatran exposure similar to that observed in severe renal impairment. Reduce the dosage of PRADAXA Capsules to 75 mg twice daily [see Warnings and Precautions (5.5), Drug Interactions (7.1), and Clinical Pharmacology (12.3)].

Treatment and Reduction in the Risk of Recurrence of Deep Venous Thrombosis and Pulmonary Embolism

Dosing recommendations for patients with CrCl ≤ 30 mL/min cannot be provided. Avoid use of concomitant P-gp inhibitors in patients with CrCl < 50 mL/min [see Warnings and Precautions (5.5), Drug Interactions (7.2) and Clinical Pharmacology (12.3)].

Prophylaxis of Deep Vein Thrombosis and Pulmonary Embolism Following Hip Replacement Surgery

Dosing recommendations for patients with CrCl ≤ 30 mL/min or on dialysis cannot be provided. Avoid use of concomitant P-gp inhibitors in patients with CrCl < 50 mL/min [see Dosage and Administration (2.5), Warnings and Precautions (5.5), Drug Interactions (7.3), and Clinical Pharmacology (12.2, 12.3)].

Pediatric patients with renal impairment

Treatment and reduction in risk of recurrence of VTE in pediatric patients

Due to lack of data in pediatric patients with eGFR < 50 mL/min/1.73 m^2 and the risk of increased exposure, avoid use of PRADAXA Capsules in these patients. Prior to the initiation of treatment with PRADAXA Capsules, estimate the glomerular filtration rate (eGFR) using the Schwartz formula: eGFR (Schwartz) = (0.413 × height in cm) / serum creatinine in mg/dL.

Treat patients with an eGFR > 50 mL/min/1.73 m^2 with the dosage according to Table 1 [see Dosage and Administration (2.3)].

2.5 Administration

PRADAXA Capsules should be swallowed whole. PRADAXA Capsules should be taken with a full glass of water. Breaking, chewing, or emptying the contents of the capsule can result in increased exposure [see Clinical Pharmacology (12.3)].

If a dose of PRADAXA Capsules is not taken at the scheduled time, the dose should be taken as soon as possible on the same day; the missed dose should be skipped if it cannot be taken at least 6 hours before the next scheduled dose. The dose of PRADAXA Capsules should not be doubled to make up for a missed dose.

Consider administration with food if gastrointestinal distress occurs with PRADAXA Capsules.

2.6 Converting from or to Warfarin

When converting patients from warfarin therapy to PRADAXA Capsules, discontinue warfarin and start PRADAXA Capsules when the INR is below 2.0.

When converting from PRADAXA Capsules to warfarin, adjust the starting time of warfarin as follows:

Adults

- For CrCl ≥ 50 mL/min, start warfarin 3 days before discontinuing PRADAXA Capsules.
- For CrCl 30-50 mL/min, start warfarin 2 days before discontinuing PRADAXA Capsules.
- For CrCl 15-30 mL/min, start warfarin 1 day before discontinuing PRADAXA Capsules.
- For CrCl < 15 mL/min, no recommendations can be made.

Pediatrics

- For eGFR ≥ 50 mL/min/1.73 m^2, start warfarin 3 days before discontinuing PRADAXA Capsules.
- Pediatric patients with an eGFR < 50 mL/min/1.73 m^2 have not been studied. Avoid use of PRADAXA Capsules in these patients.

Because PRADAXA Capsules can increase INR, the INR will better reflect warfarin's effect only after PRADAXA Capsules has been stopped for at least 2 days [see Clinical Pharmacology (12.2)].

2.7 Converting from or to Parenteral Anticoagulants

For adult and pediatric patients currently receiving a parenteral anticoagulant, start PRADAXA Capsules 0 to 2 hours before the time that the next dose of the parenteral drug was to have been administered or at the time of discontinuation of a continuously administered parenteral drug (e.g., intravenous unfractionated heparin).

For adult patients currently taking PRADAXA Capsules wait 12 hours (CrCl ≥ 30 mL/min) or 24 hours (CrCl < 30 mL/min) after the last dose of PRADAXA Capsules before initiating treatment with a parenteral anticoagulant [see Clinical Pharmacology (12.3)].

For pediatric patients currently taking PRADAXA, wait 12 hours after the last dose before switching to a parenteral anticoagulant.

2.8 Discontinuation for Surgery and Other Interventions

If possible, discontinue PRADAXA Capsules in adults 1 to 2 days (CrCl ≥ 50 mL/min) or 3 to 5 days (CrCl < 50 mL/min) before invasive or surgical procedures because of the increased risk of bleeding. Consider longer times for patients undergoing major surgery, spinal puncture, or placement of a spinal or epidural catheter or port, in whom complete hemostasis may be required [see Use in Specific Populations (8.6) and Clinical Pharmacology (12.3)].

For pediatric patients, discontinue PRADAXA Capsules 24 hours before an elective surgery (eGFR > 80 mL/min/1.73 m^2) or 2 days before an elective surgery (eGFR 50-80 mL/min/1.73 m^2). Pediatric patients with an eGFR <50 mL/min/1.73 m^2 have not been studied, avoid use of PRADAXA Capsules in these patients.

If surgery cannot be delayed, there is an increased risk of bleeding [see Warnings and Precautions (5.2)]. This risk of bleeding should be weighed against the urgency of intervention [see Warnings and Precautions (5.1, 5.3)]. Use a specific reversal agent (idarucizumab) in case of emergency surgery or urgent procedures when reversal of the anticoagulant effect of dabigatran is needed in adults. Efficacy and safety of idarucizumab have not been established in pediatric patients [see Warnings and Precautions (5.2)]. Refer to the idarucizumab prescribing information for additional information. Restart PRADAXA Capsules as soon as medically appropriate.

3 DOSAGE FORMS AND STRENGTHS

150 mg capsules with a light blue opaque cap imprinted in black with the Boehringer Ingelheim company symbol and a white opaque body imprinted in black with "R150".

110 mg capsules with a light blue opaque cap imprinted in black with the Boehringer Ingelheim company symbol and a light blue opaque body imprinted in black with "R110".

75 mg capsules with a white opaque cap imprinted in black with the Boehringer Ingelheim company symbol and a white opaque body imprinted in black with "R75".

4 CONTRAINDICATIONS

PRADAXA is contraindicated in patients with:

- Active pathological bleeding [see Warnings and Precautions (5.2) and Adverse Reactions (6.1)]
- History of a serious hypersensitivity reaction to dabigatran, dabigatran etexilate, or to one of the excipients of the product (e.g., anaphylactic reaction or anaphylactic shock) [see Adverse Reactions (6.1)]
- Mechanical prosthetic heart valve [see Warnings and Precautions (5.4)]

5 WARNINGS AND PRECAUTIONS

5.1 Increased Risk of Thrombotic Events after Premature Discontinuation

Premature discontinuation of any oral anticoagulant, including PRADAXA, in the absence of adequate alternative anticoagulation increases the risk of thrombotic events. If PRADAXA Capsules is discontinued for a reason other than pathological bleeding or completion of a course of therapy, consider coverage with another anticoagulant and restart PRADAXA Capsules as soon as medically appropriate [see Dosage and Administration (2.6, 2.7, 2.8)].

5.2 Risk of Bleeding

PRADAXA increases the risk of bleeding and can cause significant and, sometimes, fatal bleeding. Promptly evaluate any signs or symptoms of blood loss (e.g., a drop in hemoglobin and/or hematocrit or hypotension). Discontinue PRADAXA Capsules in patients with active pathological bleeding [see Dosage and Administration (2.4)].

Risk factors for bleeding include the concomitant use of other drugs that increase the risk of bleeding (e.g., anti-platelet agents, heparin, fibrinolytic therapy, and chronic use of NSAIDs). PRADAXA's anticoagulant activity and half-life are increased in patients with renal impairment [see Clinical Pharmacology (12.2)].

Reversal of Anticoagulant Effect

In adults, a specific reversal agent (idarucizumab) for PRADAXA is available when reversal of the anticoagulant effect of dabigatran is needed:

- For emergency surgery/urgent procedures
- In life-threatening or uncontrolled bleeding

In pediatric patients, the efficacy and safety of idarucizumab have not been established.

Hemodialysis can remove dabigatran; however the clinical experience supporting the use of hemodialysis as a treatment for bleeding is limited [see Overdosage (10)]. Prothrombin complex concentrates, or recombinant Factor VIIa may be considered but their use has not been evaluated in clinical trials. Protamine sulfate and vitamin K are not expected to affect the anticoagulant activity of dabigatran. Consider administration of platelet concentrates in cases where thrombocytopenia is present or long-acting antiplatelet drugs have been used.

5.3 Spinal/Epidural Anesthesia or Puncture

When neuraxial anesthesia (spinal/epidural anesthesia) or spinal puncture is employed, patients treated with anticoagulant agents are at risk of developing an epidural or spinal hematoma which can result in long-term or permanent paralysis [see Boxed Warning].

To reduce the potential risk of bleeding associated with the concurrent use of PRADAXA and epidural or spinal anesthesia/analgesia or spinal puncture, consider the pharmacokinetic profile of dabigatran [see Clinical Pharmacology (12.3)]. Placement or removal of an epidural catheter or lumbar puncture is best performed when the anticoagulant effect of dabigatran is low; however, the exact timing to reach a sufficiently low anticoagulant effect in each patient is not known.

Should the physician decide to administer anticoagulation in the context of epidural or spinal anesthesia/analgesia or lumbar puncture, monitor frequently to detect any signs or symptoms of neurological impairment, such as midline back pain, sensory and motor deficits (numbness, tingling, or weakness in lower limbs), bowel and/or bladder dysfunction. Instruct patients to immediately report if they experience any of the above signs or symptoms. If signs or symptoms of spinal hematoma are suspected, initiate urgent diagnosis and treatment including consideration for spinal cord decompression even though such treatment may not prevent or reverse neurological sequelae.

5.4 Thromboembolic and Bleeding Events in Patients with Prosthetic Heart Valves

The safety and efficacy of PRADAXA Capsules in adult patients with bileaflet mechanical prosthetic heart valves was evaluated in the RE-ALIGN trial, in which patients with bileaflet mechanical prosthetic heart valves (recently implanted or implanted more than three months prior to enrollment) were randomized to dose-adjusted warfarin or 150 mg, 220 mg, or 300 mg of PRADAXA Capsules twice a day. RE-ALIGN was terminated early due to the occurrence of significantly more thromboembolic events (valve thrombosis, stroke, transient ischemic attack, and myocardial infarction) and an excess of major bleeding (predominantly post-operative pericardial effusions requiring intervention for hemodynamic compromise) in the PRADAXA Capsules treatment arm as compared to the warfarin treatment arm. These bleeding and thromboembolic events were seen both in patients who were initiated on PRADAXA Capsules postoperatively within three days of mechanical bileaflet valve implantation, as well as in patients whose valves had been implanted more than three months prior to enrollment. Therefore, the use of PRADAXA is contraindicated in all patients with mechanical prosthetic valves [see Contraindications (4)].

The use of PRADAXA for the prophylaxis of thromboembolic events in patients with atrial fibrillation in the setting of other forms of valvular heart disease, including the presence of a bioprosthetic heart valve, has not been studied and is not recommended.

5.5 Effect of P-gp Inducers and Inhibitors on Dabigatran Exposure

The concomitant use of PRADAXA with P-gp inducers (e.g., rifampin) reduces exposure to dabigatran and should generally be avoided [see Clinical Pharmacology (12.3)].

P-gp inhibition and impaired renal function are the major independent factors that result in increased exposure to dabigatran [see Clinical Pharmacology (12.3)]. Concomitant use of P-gp inhibitors in patients with renal impairment is expected to produce increased exposure of dabigatran compared to that seen with either factor alone.

Reduction of Risk of Stroke and Systemic Embolism in Non-valvular Atrial Fibrillation in Adult Patients

Reduce the dosage of PRADAXA Capsules to 75 mg twice daily when dronedarone or systemic ketoconazole is co-administered with PRADAXA Capsules in patients with moderate renal impairment (CrCl 30-50 mL/min). Avoid use of PRADAXA Capsules and P-gp inhibitors in patients with severe renal impairment (CrCl 15-30 mL/min) [see Drug Interactions (7.1) and Use in Specific Populations (8.6)].

Treatment and Reduction in the Risk of Recurrence of Deep Venous Thrombosis and Pulmonary Embolism in Adult Patients

Avoid use of PRADAXA Capsules and concomitant P-gp inhibitors in patients with CrCl < 50 mL/min [see Drug Interactions (7.2) and Use in Specific Populations (8.6)].

Prophylaxis of Deep Vein Thrombosis and Pulmonary Embolism in Adult Patients Following Hip Replacement Surgery

Avoid use of PRADAXA Capsules and concomitant P-gp inhibitors in patients with CrCl < 50 mL/min [see Drug Interactions (7.3) and Use in Specific Populations (8.6)].

Treatment and reduction in risk of recurrence of VTE in pediatric patients

The concomitant use of PRADAXA Capsules with P-gp-inhibitors has not been studied in pediatric patients but may increase exposure to dabigatran.

5.6 Increased Risk of Thrombosis in Patients with Triple-Positive Antiphospholipid Syndrome

Direct-acting oral anticoagulants (DOACs), including PRADAXA, are not recommended for use in patients with triple-positive antiphospholipid syndrome (APS). For patients with APS (especially those who are triple-positive [positive for lupus anticoagulant, anticardiolipin, and anti-beta 2-glycoprotein I antibodies]), treatment with DOACs has been associated with increased rates of recurrent thrombotic events compared with vitamin K antagonist therapy.

6 ADVERSE REACTIONS

The following clinically significant adverse reactions are described elsewhere in the labeling:

- Increased Risk of Thrombotic Events after Premature Discontinuation [see Warnings and Precautions (5.1)]
- Risk of Bleeding [see Warnings and Precautions (5.2)]
- Spinal/Epidural Anesthesia or Puncture [see Warnings and Precautions (5.3)]
- Thromboembolic and Bleeding Events in Patients with Prosthetic Heart Valves [see Warnings and Precautions (5.4)]
- Increased Risk of Thrombosis in Patients with Triple-Positive Antiphospholipid Syndrome [see Warnings and Precautions (5.6)]

The most serious adverse reactions reported with PRADAXA were related to bleeding [see Warnings and Precautions (5.2)].

6.1 Clinical Trials Experience

Because clinical trials are conducted under widely varying conditions, adverse reactions rates observed in the clinical trials of a drug cannot be directly compared to rates in the clinical trials of another drug and may not reflect the rates observed in practice.

Adult Trials

Reduction of Risk of Stroke and Systemic Embolism in Non-valvular Atrial Fibrillation

The RE-LY (Randomized Evaluation of Long-term Anticoagulant Therapy) study provided safety information on the use of two doses of PRADAXA Capsules and warfarin [see Clinical Studies (14.1)]. The numbers of patients and their exposures are described in Table 2. Limited information is presented on the 110 mg dosing arm because this dose is not approved.

Table 2 Summary of Treatment Exposure in RE-LY
 | PRADAXA Capsules 110 mg twice daily | PRADAXA Capsules 150 mg twice daily | Warfarin
Total number treated | 5,983 | 6,059 | 5,998
Exposure
> 12 months | 4,936 | 4,939 | 5,193
> 24 months | 2,387 | 2,405 | 2,470
Mean exposure (months) | 20.5 | 20.3 | 21.3
Total patient-years | 10,242 | 10,261 | 10,659

Drug Discontinuation in RE-LY

The rates of adverse reactions leading to treatment discontinuation were 21% for PRADAXA Capsules 150 mg and 16% for warfarin. The most frequent adverse reactions leading to discontinuation of PRADAXA Capsules were bleeding and gastrointestinal events (i.e., dyspepsia, nausea, upper abdominal pain, gastrointestinal hemorrhage, and diarrhea).

Bleeding [see Warnings and Precautions (5.2)]

Table 3 shows the number of adjudicated major bleeding events during the treatment period in the RE-LY study, with the bleeding rate per 100 subject-years (%). Major bleeding is defined as bleeding accompanied by one or more of the following: a decrease in hemoglobin of ≥ 2 g/dL, a transfusion of ≥ 2 units of packed red blood cells, bleeding at a critical site or with a fatal outcome. Intracranial hemorrhage included intracerebral (hemorrhagic stroke), subarachnoid, and subdural bleeds.

Table 3 Adjudicated Major Bleeding Events in Treated Patientsa
Event | PRADAXA Capsules 150 mg N = 6,059 n (%/yearb) | Warfarin N = 5,998 n (%/yearb) | PRADAXA Capsules 150 mg vs Warfarin HR (95% CI)
Major Bleedingc | 350 (3.47) | 374 (3.58) | 0.97 (0.84, 1.12)
Intracranial Hemorrhage (ICH)d | 23 (0.22) | 82 (0.77) | 0.29 (0.18, 0.46)
Hemorrhagic Strokee | 6 (0.06) | 40 (0.37) | 0.16 (0.07, 0.37)
Other ICH | 17 (0.17) | 46 (0.43) | 0.38 (0.22, 0.67)
Gastrointestinal | 162 (1.59) | 111 (1.05) | 1.51 (1.19, 1.92)
Fatal Bleedingf | 7 (0.07) | 16 (0.15) | 0.45 (0.19, 1.10)
ICH | 3 (0.03) | 9 (0.08) | 0.35 (0.09, 1.28)
Non-intracranialg | 4 (0.04) | 7 (0.07) | 0.59 (0.17, 2.02)
aPatients during treatment or within 2 days of stopping study treatment. Major bleeding events within each subcategory were counted once per patient, but patients may have contributed events to multiple subcategories.
bAnnual event rate per 100 pt-years = 100 * number of subjects with event/subject-years. Subject-years is defined as cumulative number of days from first drug intake to event date, date of last drug intake + 2, death date (whatever occurred first) across all treated subjects divided by 365.25. In case of recurrent events of the same category, the first event was considered.
cDefined as bleeding accompanied by one or more of the following: a decrease in hemoglobin of ≥ 2 g/dL, a transfusion of 2 or more units of packed red blood cells, bleeding at a critical site or with fatal outcome.
dIntracranial bleed included intracerebral (hemorrhagic stroke), subarachnoid, and subdural bleeds.
eOn-treatment analysis based on the safety population, compared to ITT analysis presented in Section 14 Clinical Studies.
fFatal bleed: Adjudicated major bleed as defined above with investigator reported fatal outcome and adjudicated death with primary cause from bleeding.
gNon-intracranial fatal bleed: Adjudicated major bleed as defined above and adjudicated death with primary cause from bleeding but without symptomatic intracranial bleed based on investigator's clinical assessment.

There was a higher rate of any gastrointestinal bleeds in patients receiving PRADAXA Capsules 150 mg than in patients receiving warfarin (6.6% vs 4.2%, respectively).

The risk of major bleeds was similar with PRADAXA Capsules 150 mg and warfarin across major subgroups defined by baseline characteristics (see Figure 1), with the exception of age, where there was a trend toward a higher incidence of major bleeding on PRADAXA Capsules (hazard ratio 1.2, 95% CI: 1.0 to 1.5) for patients ≥ 75 years of age.

Figure 1 Adjudicated Major Bleeding by Baseline Characteristics Including Hemorrhagic Stroke Treated Patients

Note: The figure above presents effects in various subgroups all of which are baseline characteristics and all of which were pre-specified. The 95% confidence limits that are shown do not take into account how many comparisons were made, nor do they reflect the effect of a particular factor after adjustment for all other factors. Apparent homogeneity or heterogeneity among groups should not be over-interpreted.

Gastrointestinal Adverse Reactions

Patients on PRADAXA Capsules 150 mg had an increased incidence of gastrointestinal adverse reactions (35% vs 24% on warfarin). These were commonly dyspepsia (including abdominal pain upper, abdominal pain, abdominal discomfort, and epigastric discomfort) and gastritis-like symptoms (including GERD, esophagitis, erosive gastritis, gastric hemorrhage, hemorrhagic gastritis, hemorrhagic erosive gastritis, and gastrointestinal ulcer).

Hypersensitivity Reactions

In the RE-LY study, drug hypersensitivity (including urticaria, rash, and pruritus), allergic edema, anaphylactic reaction, and anaphylactic shock were reported in < 0.1% of patients receiving PRADAXA Capsules.

Treatment and Reduction in the Risk of Recurrence of Deep Venous Thrombosis and Pulmonary Embolism

PRADAXA Capsules was studied in 4,387 patients in 4 pivotal, parallel, randomized, double-blind trials. Three of these trials were active-controlled (warfarin) (RE-COVER, RE-COVER II, and RE-MEDY), and one study (RE-SONATE) was placebo-controlled. The demographic characteristics were similar among the 4 pivotal studies and between the treatment groups within these studies. Approximately 60% of the treated patients were male, with a mean age of 55.1 years. The majority of the patients were white (87.7%), 10.3% were Asian, and 1.9% were black with a mean CrCl of 105.6 mL/min.

Bleeding events for the 4 pivotal studies were classified as major bleeding events if at least one of the following criteria applied: fatal bleeding, symptomatic bleeding in a critical area or organ (intraocular, intracranial, intraspinal or intramuscular with compartment syndrome, retroperitoneal bleeding, intra-articular bleeding, or pericardial bleeding), bleeding causing a fall in hemoglobin level of 2.0 g/dL (1.24 mmol/L or more, or leading to transfusion of 2 or more units of whole blood or red cells).

RE-COVER and RE-COVER II studies compared PRADAXA Capsules 150 mg twice daily and warfarin for the treatment of deep vein thrombosis and pulmonary embolism. Patients received 5-10 days of an approved parenteral anticoagulant therapy followed by 6 months, with mean exposure of 164 days, of oral only treatment; warfarin was overlapped with parenteral therapy. Table 4 shows the number of patients experiencing bleeding events in the pooled analysis of RE-COVER and RE-COVER II studies during the full treatment including parenteral and oral only treatment periods after randomization.

Table 4 Bleeding Events in RE-COVER and RE-COVER II Treated Patients
 | Bleeding Events—Full Treatment Period Including Parenteral Treatment
 | PRADAXA Capsules 150 mg twice daily N (%) | Warfarin N (%) | Hazard Ratio (95% CI)c
Patients | N=2,553 | N=2,554
Major bleeding eventa | 37 (1.4) | 51 (2.0) | 0.73 (0.48, 1.11)
Fatal bleeding | 1 (0.04) | 2 (0.1)
Bleeding in a critical area or organ | 7 (0.3) | 15 (0.6)
Fall in hemoglobin ≥ 2 g/dL or transfusion ≥ 2 units of whole blood or packed red blood cells | 32 (1.3) | 38 (1.5)
Bleeding sites for MBEb
Intracranial | 2 (0.1) | 5 (0.2)
Retroperitoneal | 2 (0.1) | 1 (0.04)
Intraarticular | 2 (0.1) | 4 (0.2)
Intramuscular | 2 (0.1) | 6 (0.2)
Gastrointestinal | 15 (0.6) | 14 (0.5)
Urogenital | 7 (0.3) | 14 (0.5)
Other | 8 (0.3) | 8 (0.3)
Clinically relevant non-major bleeding | 101 (4.0) | 170 (6.7) | 0.58 (0.46, 0.75)
Any bleeding | 411 (16.1) | 567 (22.7) | 0.70 (0.61, 0.79)
Note: MBE can belong to more than one criterion.
aPatients with at least one MBE.
bBleeding site based on investigator assessment. Patients can have more than one site of bleeding.
cConfidence interval

The rate of any gastrointestinal bleeds in patients receiving PRADAXA Capsules 150 mg in the full treatment period was 3.1% (2.4% on warfarin).

The RE-MEDY and RE-SONATE studies provided safety information on the use of PRADAXA Capsules for the reduction in the risk of recurrence of deep vein thrombosis and pulmonary embolism.

RE-MEDY was an active-controlled study (warfarin) in which 1,430 patients received PRADAXA Capsules 150 mg twice daily following 3 to 12 months of oral anticoagulant regimen. Patients in the treatment studies who rolled over into the RE-MEDY study had a combined treatment duration of up to more than 3 years, with mean exposure of 473 days. Table 5 shows the number of patients experiencing bleeding events in the study.

Table 5 Bleeding Events in RE-MEDY Treated Patients
 | PRADAXA Capsules 150 mg twice daily N (%) | Warfarin N (%) | Hazard Ratio (95% CI)c
Patients | N=1,430 | N=1,426
Major bleeding eventa | 13 (0.9) | 25 (1.8) | 0.54 (0.25, 1.16)
Fatal bleeding | 0 | 1 (0.1)
Bleeding in a critical area or organ | 7 (0.5) | 11 (0.8)
Fall in hemoglobin ≥ 2 g/dL or transfusion ≥ 2 units of whole blood or packed red blood cells | 7 (0.5) | 16 (1.1)
Bleeding sites for MBEb
Intracranial | 2 (0.1) | 4 (0.3)
Intraocular | 4 (0.3) | 2 (0.1)
Retroperitoneal | 0 | 1 (0.1)
Intraarticular | 0 | 2 (0.1)
Intramuscular | 0 | 4 (0.3)
Gastrointestinal | 4 (0.3) | 8 (0.6)
Urogenital | 1 (0.1) | 1 (0.1)
Other | 2 (0.1) | 4 (0.3)
Clinically relevant non-major bleeding | 71 (5.0) | 125 (8.8) | 0.56 (0.42, 0.75)
Any bleeding | 278 (19.4) | 373 (26.2) | 0.71 (0.61, 0.83)
Note: MBE can belong to more than one criterion.
aPatients with at least one MBE.
bBleeding site based on investigator assessment. Patients can have more than one site of bleeding.
cConfidence interval

In the RE-MEDY study, the rate of any gastrointestinal bleeds in patients receiving PRADAXA Capsules 150 mg was 3.1% (2.2% on warfarin).

RE-SONATE was a placebo-controlled study in which 684 patients received PRADAXA Capsules 150 mg twice daily following 6 to 18 months of oral anticoagulant regimen. Patients in the treatment studies who rolled over into the RE-SONATE study had combined treatment duration up to 9 months, with mean exposure of 165 days. Table 6 shows the number of patients experiencing bleeding events in the study.

Table 6 Bleeding Events in RE-SONATE Treated Patients
 | PRADAXA Capsules 150 mg twice daily N (%) | Placebo N (%) | Hazard Ratio (95% CI)c
Patients | N=684 | N=659
Major bleeding eventa | 2 (0.3) | 0
Bleeding in a critical area or organ | 0 | 0
Gastrointestinalb | 2 (0.3) | 0
Clinically relevant non-major bleeding | 34 (5.0) | 13 (2.0) | 2.54 (1.34, 4.82)
Any bleeding | 72 (10.5) | 40 (6.1) | 1.77 (1.20, 2.61)
Note: MBE can belong to more than one criterion.
aPatients with at least one MBE.
bBleeding site based on investigator assessment. Patients can have more than one site of bleeding.
cConfidence interval

In the RE-SONATE study, the rate of any gastrointestinal bleeds in patients receiving PRADAXA Capsules 150 mg was 0.7% (0.3% on placebo).

Clinical Myocardial Infarction Events

In the active-controlled VTE studies, a higher rate of clinical myocardial infarction was reported in patients who received PRADAXA Capsules [20 (0.66 per 100 patient-years)] than in those who received warfarin [5 (0.17 per 100 patient-years)]. In the placebo-controlled study, a similar rate of nonfatal and fatal clinical myocardial infarction was reported in patients who received PRADAXA Capsules [1 (0.32 per 100 patient-years)] and in those who received placebo [1 (0.34 per 100 patient-years)].

Gastrointestinal Adverse Reactions

In the four pivotal studies, patients on PRADAXA Capsules 150 mg had a similar incidence of gastrointestinal adverse reactions (24.7% vs 22.7% on warfarin). Dyspepsia (including abdominal pain upper, abdominal pain, abdominal discomfort, and epigastric discomfort) occurred in patients on PRADAXA Capsules 7.5% vs 5.5% on warfarin, and gastritis-like symptoms (including gastritis, GERD, esophagitis, erosive gastritis and gastric hemorrhage) occurred at 3.0% vs 1.7%, respectively.

Hypersensitivity Reactions

In the 4 pivotal studies, drug hypersensitivity (including urticaria, rash, and pruritus), allergic edema, anaphylactic reaction, and anaphylactic shock were reported in 0.1% of patients receiving PRADAXA Capsules.

Prophylaxis of Deep Vein Thrombosis and Pulmonary Embolism Following Hip Replacement Surgery

PRADAXA Capsules was studied in 5,476 patients, randomized and treated in two double-blind, active-controlled non-inferiority trials (RE-NOVATE and RE-NOVATE II). The demographic characteristics were similar across the two studies and between the treatment groups within these studies. Approximately 45.3% of the treated patients were male, with a mean age of 63.2 years. The majority of the patients were white (96.1%), 3.6% were Asian, and 0.3% were black with a mean CrCl of 92 mL/min.

Bleeding events for the RE-NOVATE and RE-NOVATE II studies were classified as major bleeding events if at least one of the following criteria applied: fatal bleeding, symptomatic bleeding in a critical area or organ (intraocular, intracranial, intraspinal or retroperitoneal bleeding), bleeding causing a fall in hemoglobin level of 2.0 g/dL (1.24 mmol/L) or more, or leading to transfusion of 2 or more units of whole blood or red cells, requiring treatment cessation or leading to re-operation.

The RE-NOVATE study compared PRADAXA Capsules 75 mg taken orally 1-4 hours after surgery followed by 150 mg once daily, PRADAXA Capsules 110 mg taken orally 1-4 hours after surgery followed by 220 mg once daily and subcutaneous enoxaparin 40 mg once daily initiated the evening before surgery for the prophylaxis of deep vein thrombosis and pulmonary embolism in patients who had undergone hip replacement surgery. The RE-NOVATE II study compared PRADAXA Capsules 110 mg taken orally 1-4 hours after surgery followed by 220 mg once daily and subcutaneous enoxaparin 40 mg once daily initiated the evening before surgery for the prophylaxis of deep vein thrombosis and pulmonary embolism in patients who had undergone hip replacement surgery. In the RE-NOVATE and RE-NOVATE II studies, patients received 28-35 days of PRADAXA Capsules or enoxaparin with median exposure of 33 days. Tables 7 and 8 show the number of patients experiencing bleeding events in the analysis of RE-NOVATE and RE-NOVATE II.

Table 7 Bleeding Events in RE-NOVATE Treated Patients
 | PRADAXA Capsules 220 mg N (%) | Enoxaparin N (%)
Patients | N=1,146 | N=1,154
Major bleeding event | 23 (2.0) | 18 (1.6)
Clinically relevant non-major bleeding | 48 (4.2) | 40 (3.5)
Any bleeding | 141 (12.3) | 132 (11.4)

Table 8 Bleeding Events in RE-NOVATE II Treated Patients
 | PRADAXA Capsules 220 mg N (%) | Enoxaparin N (%)
Patients | N=1,010 | N=1,003
Major bleeding event | 14 (1.4) | 9 (0.9)
Clinically relevant non-major bleeding | 26 (2.6) | 20 (2.0)
Any bleeding | 98 (9.7) | 83 (8.3)

In the two studies, the rate of major gastrointestinal bleeds in patients receiving PRADAXA Capsules and enoxaparin was the same (0.1%) and for any gastrointestinal bleeds was 1.4% for PRADAXA Capsules 220 mg and 0.9% for enoxaparin.

Gastrointestinal Adverse Reactions

In the two studies, the incidence of gastrointestinal adverse reactions for patients on PRADAXA Capsules 220 mg and enoxaparin was 39.5% and 39.5%, respectively. Dyspepsia (including abdominal pain upper, abdominal pain, abdominal discomfort, and epigastric discomfort) occurred in patients on PRADAXA Capsules 220 mg in 4.1% vs. 3.8% on enoxaparin, and gastritis-like symptoms (including gastritis, GERD, esophagitis, erosive gastritis and gastric hemorrhage) occurred at 0.6% vs 1.0%, respectively.

Hypersensitivity Reactions

In the two studies, drug hypersensitivity (such as urticaria, rash, and pruritus) was reported in 0.3% of patients receiving PRADAXA Capsules 220 mg.

Clinical Myocardial Infarction Events

In the two studies, clinical myocardial infarction was reported in 2 (0.1%) of patients who received PRADAXA Capsules 220 mg and 6 (0.3%) of patients who received enoxaparin.

Pediatric Trials

Treatment of VTE in Pediatric Patients

The safety of PRADAXA in the treatment of VTE in pediatric patients was studied in one phase III trial (DIVERSITY). The DIVERSITY study was a randomized, open-label, active-controlled, parallel-group trial comparing PRADAXA with standard of care – SOC (vitamin K antagonists, low molecular weight heparin, or fondaparinux). There were 266 pediatric patients who received study treatment, 176 patients treated with PRADAXA and 90 patients treated with SOC. Patients on PRADAXA received age- and weight-adjusted dosages of an age-appropriate formulation of PRADAXA (capsules, pellets, or oral solution) twice daily.

Patients had a median age of 14 years (range: 0-17 years), 92% were white, and half the patients were male (50%). Following at least 5 days of parenteral anticoagulant therapy, the median duration of treatment with PRADAXA was 85 days (range: 1-105). Patients with estimated glomerular filtration rate (eGFR) < 50 mL/min/1.73m^2 were excluded from the trial.

Bleeding

Data on adjudicated major bleeding, clinically relevant non-major (CRNM) bleeding and minor bleeding events, for the PRADAXA group and the SOC group in the DIVERSITY study, are reported in Table 9. There was no statistically significant difference in the time to first major bleeding event.

Table 9 Summary of All Adjudicated Bleeding Events During On-Treatment Period in DIVERSITY
 | PRADAXA N (%) | Standard of Care (SOC) N (%)
Patients | N=176 | N=90
Major bleeding event^1 | 4 (2.3) | 2 (2.2)
Fatal bleeding | 0 | 1 (1.1)
Clinically relevant non-major bleeding | 2 (1.1) | 1 (1.1)
Minor bleeding | 33 (19) | 21 (23)
Major and clinically relevant non-major bleeding | 6 (3.4) | 3 (3.3)
Any bleeding | 38 (22) | 22 (24)
^1 Major bleeding event if at least one of the following criteria applied: fatal bleeding, symptomatic bleeding in a critical area or organ (intraocular, intracranial, intraspinal or intramuscular with compartment syndrome, retroperitoneal bleeding, intra-articular bleeding, or pericardial bleeding), bleeding causing a fall in hemoglobin level of 2.0 g/dL (1.24 mmol/L) or more, or leading to transfusion of 2 or more units of whole blood or red cells.

Site-specific bleeding rates were comparable between the two arms, with the exception of the rate of any gastrointestinal bleeds (5.7% in PRADAXA arm vs 1.8% in SOC arm).

Gastrointestinal Adverse Reactions

The incidence of gastrointestinal adverse reactions for patients on PRADAXA and SOC was 32% and 12%, respectively, with the following occurring in ≥ 5% of patients taking PRADAXA: dyspepsia (including term gastro-esophageal reflux disease, gastric pH decreased and esophagitis) in 9% (vs 2%), upper abdominal pain in 5% (vs 1%), vomiting in 8% (vs 2%), nausea 5% (vs 4%), and diarrhea 5% (vs 1%).

Reduction in Risk of Recurrence of VTE in Pediatric Patients

The safety of PRADAXA in the reduction in the risk of recurrence of VTE in pediatric patients was studied in one open-label single-arm trial (Study 2). Study 2 enrolled patients who required further anticoagulation due to the presence of a clinical risk factor after completing the initial treatment for confirmed VTE (for at least 3 months) or after completing the DIVERSITY study and received PRADAXA until the clinical risk factor resolved, or up to a maximum of 12 months. There were 213 pediatric patients treated with PRADAXA, in a similar fashion as in the DIVERSITY trial.

Patients had a median age of 14 years (range: 0-18 years), 91% were white, and 55% of patients were male. Patients previously enrolled on DIVERSITY accounted for 43% of patients enrolled on Study 2 (29% from PRADAXA arm and 14% from SOC arm). The median duration of treatment with PRADAXA in Study 2 was 42 weeks (range: 0-56 weeks), with 45% of patients completing the 12-month planned duration, 17% stopping due to resolution of VTE risk factors, 12% stopping due to failure to attain target dabigatran concentration and 6% had an adverse event leading to discontinuation.

During the on-treatment period of Study 2, 3 patients (1.4%) had a major bleeding event, 3 patients (1.4%) had a clinically relevant non-major bleeding event, and 44 patients (20%) had a minor bleeding event. The most common drug-related adverse reactions were dyspepsia (5%), epistaxis (3.3%), nausea (3.3%) and menorrhagia (2.8%).

The adverse reaction profile in pediatric patients was generally consistent with that of adult patients.

6.2 Postmarketing Experience

The following adverse reactions have been identified during post approval use of PRADAXA. Because these reactions are reported voluntarily from a population of uncertain size, it is not always possible to reliably estimate their frequency or establish a causal relationship to drug exposure.

Blood and Lymphatic System Disorders: Agranulocytosis, neutropenia, thrombocytopenia
Gastrointestinal Disorders: Esophageal ulcer
Immune System Disorders: Angioedema
Renal and Urinary Disorders: Anticoagulant-related nephropathy
Skin and Subcutaneous Tissue Disorders: Alopecia

7 DRUG INTERACTIONS

7.1 Reduction of Risk of Stroke and Systemic Embolism in Non-valvular Atrial Fibrillation in Adult Patients

The concomitant use of PRADAXA with P-gp inducers (e.g., rifampin) reduces exposure to dabigatran and should generally be avoided [see Clinical Pharmacology (12.3)].

P-gp inhibition and impaired renal function are the major independent factors that result in increased exposure to dabigatran [see Clinical Pharmacology (12.3)]. Concomitant use of P-gp inhibitors in patients with renal impairment is expected to produce increased exposure of dabigatran compared to that seen with either factor alone.

In patients with moderate renal impairment (CrCl 30-50 mL/min), reduce the dosage of PRADAXA to 75 mg twice daily when administered concomitantly with the P-gp inhibitors dronedarone or systemic ketoconazole. The use of the P-gp inhibitors verapamil, amiodarone, quinidine, clarithromycin, and ticagrelor does not require a dosage adjustment of PRADAXA. These results should not be extrapolated to other P-gp inhibitors [see Warnings and Precautions (5.5), Use in Specific Populations (8.6), and Clinical Pharmacology (12.3)].

The concomitant use of PRADAXA and P-gp inhibitors in patients with severe renal impairment (CrCl 15-30 mL/min) should be avoided [see Warnings and Precautions (5.5), Use in Specific Populations (8.6), and Clinical Pharmacology (12.3)].

7.2 Treatment and Reduction in the Risk of Recurrence of Deep Venous Thrombosis and Pulmonary Embolism in Adult Patients

Avoid use of PRADAXA and P-gp inhibitors in patients with CrCl < 50 mL/min [see Warnings and Precautions (5.5), Use in Specific Populations (8.6), and Clinical Pharmacology (12.3)].

7.3 Prophylaxis of Deep Vein Thrombosis and Pulmonary Embolism in Adult Patients Following Hip Replacement Surgery

In patients with CrCl ≥ 50 mL/min who have concomitant administration of P-gp inhibitors such as dronedarone or systemic ketoconazole, it may be helpful to separate the timing of administration of PRADAXA and the P-gp inhibitor by several hours. The concomitant use of PRADAXA and P-gp inhibitors in patients with CrCl < 50 mL/min should be avoided [see Warnings and Precautions (5.5), Use in Specific Populations (8.6), and Clinical Pharmacology (12.2, 12.3)].

7.4 Treatment and Reduction in Risk of Recurrence of VTE in Pediatric Patients

The concomitant use of PRADAXA with P-gp inhibitors has not been studied in pediatric patients but may increase exposure to dabigatran [see Warnings and Precautions (5.5)].

8 USE IN SPECIFIC POPULATIONS

8.1 Pregnancy

Risk Summary

The limited available data on PRADAXA use in pregnant women are insufficient to determine drug-associated risks for adverse developmental outcomes. There are risks to the mother associated with untreated venous thromboembolism in pregnancy and a risk of hemorrhage in the mother and fetus associated with the use of anticoagulants (see Clinical Considerations). In pregnant rats treated from implantation until weaning, dabigatran increased the number of dead offspring and caused excess vaginal/uterine bleeding close to parturition at an exposure 2.6 times the human exposure. At a similar exposure, dabigatran decreased the number of implantations when rats were treated prior to mating and up to implantation (gestation Day 6). Dabigatran administered to pregnant rats and rabbits during organogenesis up to exposures 8 and 13 times the human exposure, respectively, did not induce major malformations. However, the incidence of delayed or irregular ossification of fetal skull bones and vertebrae was increased in the rat (see Data).

The estimated background risk of major birth defects and miscarriage for the indicated population is unknown. All pregnancies have a background risk of birth defect, loss, or other adverse outcomes. In the U.S. general population, the estimated background risk of major birth defects and miscarriage in clinically recognized pregnancies is 2%-4% and 15%-20%, respectively.

Clinical Considerations

Disease-associated maternal and/or embryo/fetal risk

Pregnancy confers an increased risk for thromboembolism that is higher for women with underlying thromboembolic disease and certain high-risk pregnancy conditions. Published data describe that women with a previous history of venous thrombosis are at high risk for recurrence during pregnancy.

Fetal/Neonatal adverse reaction

Use of anticoagulants, including PRADAXA, may increase the risk of bleeding in the fetus and neonate. Monitor neonates for bleeding [see Warnings and Precautions (5.2)].

Labor or delivery

All patients receiving anticoagulants, including pregnant women, are at risk for bleeding. PRADAXA use during labor or delivery in women who are receiving neuraxial anesthesia may result in epidural or spinal hematomas. Consider discontinuation or use of shorter acting anticoagulant as delivery approaches [see Warnings and Precautions (5.2, 5.3)].

Data

Animal Data

Dabigatran has been shown to decrease the number of implantations when male and female rats were treated at a dosage of 70 mg/kg (about 2.6 to 3.0 times the human exposure at MRHD of 300 mg/day based on area under the curve [AUC] comparisons) prior to mating and up to implantation (gestation Day 6). Treatment of pregnant rats after implantation with dabigatran at the same dose increased the number of dead offspring and caused excess vaginal/uterine bleeding close to parturition. Dabigatran administered to pregnant rats and rabbits during organogenesis up to maternally toxic doses of 200 mg/kg (8 and 13 times the human exposure, respectively, at a MRHD of 300 mg/day based on AUC comparisons) did not induce major malformations, but increased the incidence of delayed or irregular ossification of fetal skull bones and vertebrae in the rat.

Death of offspring and mother rats during labor in association with uterine bleeding occurred during treatment of pregnant rats from implantation (gestation Day 7) to weaning (lactation Day 21) with dabigatran at a dose of 70 mg/kg (about 2.6 times the human exposure at MRHD of 300 mg/day based on AUC comparisons).

8.2 Lactation

Risk Summary

There are insufficient data to assess the presence of dabigatran in human milk. There are no data on the effects of dabigatran on the breastfed child or on milk production. Dabigatran and/or its metabolites were present in rat milk. Breastfeeding is not recommended during treatment with PRADAXA.

8.3 Females and Males of Reproductive Potential

Females of reproductive potential requiring anticoagulation should discuss pregnancy planning with their physician.

The risk of clinically significant uterine bleeding, potentially requiring gynecological surgical interventions, identified with oral anticoagulants including PRADAXA should be assessed in females of reproductive potential and those with abnormal uterine bleeding.

8.4 Pediatric Use

The safety and effectiveness of PRADAXA Capsules for the treatment and the reduction in risk of recurrence of venous thromboembolism have been established in pediatric patients 8 to less than 18 years of age. Use of PRADAXA for this indication is supported by evidence from adequate and well-controlled studies in pediatric patients. These studies included an open-label, randomized, parallel-group study and an open-label, single-arm safety study [see Adverse Reactions (6.1) and Clinical Studies (14.4, 14.5)]. Other age-appropriate pediatric dosage forms of dabigatran etexilate are available for pediatric patients less than 8 years of age for these indications.

Safety and effectiveness of PRADAXA Capsules have not been established in pediatric patients with non-valvular atrial fibrillation or those who have undergone hip replacement surgery.

8.5 Geriatric Use

Of the total number of patients in the RE-LY study, 82% were 65 and over, while 40% were 75 and over. The risk of stroke and bleeding increases with age, but the risk-benefit profile is favorable in all age groups [see Warnings and Precautions (5), Adverse Reactions (6.1), and Clinical Studies (14.1)].

8.6 Renal Impairment

Reduction of Risk of Stroke and Systemic Embolism in Non-valvular Atrial Fibrillation in Adult Patients

No dose adjustment of PRADAXA is recommended in patients with mild or moderate renal impairment [see Clinical Pharmacology (12.3)]. Reduce the dose of PRADAXA in patients with severe renal impairment (CrCl 15-30 mL/min) [see Dosage and Administration (2.2, 2.4) and Clinical Pharmacology (12.3)]. Dosing recommendations for patients with CrCl < 15 mL/min or on dialysis cannot be provided.

Adjust dose appropriately in patients with renal impairment receiving concomitant P-gp inhibitors [see Warnings and Precautions (5.5), Drug Interactions (7.1), and Clinical Pharmacology (12.3)].

Treatment and Reduction in the Risk of Recurrence of Deep Venous Thrombosis and Pulmonary Embolism in Adult Patients

Patients with severe renal impairment (CrCl ≤ 30 mL/min) were excluded from RE-COVER.

Dosing recommendations for patients with CrCl ≤ 30 mL/min or on dialysis cannot be provided. Avoid use of PRADAXA with concomitant P-gp inhibitors in patients with CrCl < 50 mL/min [see Warnings and Precautions (5.5), Drug Interactions (7.2), and Clinical Pharmacology (12.3)].

Prophylaxis of Deep Vein Thrombosis and Pulmonary Embolism in Adult Patients Following Hip Replacement Surgery

Patients with severe renal impairment (CrCl < 30 mL/min) were excluded from RE-NOVATE and RE-NOVATE II.

Dosing recommendations for patients with CrCl < 30 mL/min or on dialysis cannot be provided.

Avoid use of PRADAXA with concomitant P-gp inhibitors in patients with CrCl < 50 mL/min [see Warnings and Precautions (5.5), Drug Interactions (7.3), and Clinical Pharmacology (12.2, 12.3)].

Treatment and Reduction in the Risk of Recurrence of VTE in Pediatric Patients

PRADAXA has not been studied in pediatric patients with eGFR < 50 mL/min/1.73 m^2. Reduced renal function could increase exposure. Dosing recommendations cannot be provided for treatment of these patients. Avoid use of PRADAXA Capsules in these patients [see Dosage and Administration (2.4)].

10 OVERDOSAGE

Accidental overdose may lead to hemorrhagic complications. In the event of hemorrhagic complications, initiate appropriate clinical support, discontinue treatment with PRADAXA, and investigate the source of bleeding. A specific reversal agent (idarucizumab) is available for adult patients.

Dabigatran is primarily eliminated by the kidneys with a low plasma protein binding of approximately 35%. Hemodialysis can remove dabigatran; however, data supporting this approach are limited. Using a high-flux dialyzer, blood flow rate of 200 mL/min, and dialysate flow rate of 700 mL/min, approximately 49% of total dabigatran can be cleared from plasma over 4 hours. At the same dialysate flow rate, approximately 57% can be cleared using a dialyzer blood flow rate of 300 mL/min, with no appreciable increase in clearance observed at higher blood flow rates. Upon cessation of hemodialysis, a redistribution effect of approximately 7% to 15% is seen. The effect of dialysis on dabigatran's plasma concentration would be expected to vary based on patient specific characteristics. Measurement of aPTT or ECT may help guide therapy [see Warnings and Precautions (5.2) and Clinical Pharmacology (12.2)].

11 DESCRIPTION

The chemical name for dabigatran etexilate mesylate, a direct thrombin inhibitor, is β-Alanine, N-[[2-[[[4-[[[(hexyloxy)carbonyl]amino]iminomethyl] phenyl]amino]methyl]-1-methyl-1H-benzimidazol-5-yl]carbonyl]-N-2-pyridinyl-,ethyl ester, methanesulfonate. The empirical formula is C34H41N7O5 ∙ CH4O3S and the molecular weight is 723.86 (mesylate salt), 627.75 (free base). The structural formula is:

Dabigatran etexilate mesylate is a yellow-white to yellow powder. A saturated solution in pure water has a solubility of 1.8 mg/mL. It is freely soluble in methanol, slightly soluble in ethanol, and sparingly soluble in isopropanol.

PRADAXA Capsules are supplied in 75 mg, 110 mg, and 150 mg strengths for oral administration. Each capsule contains dabigatran etexilate mesylate as the active ingredient: 150 mg dabigatran etexilate (equivalent to 172.95 mg dabigatran etexilate mesylate), 110 mg dabigatran etexilate (equivalent to 126.83 mg dabigatran etexilate mesylate), or 75 mg dabigatran etexilate (equivalent to 86.48 mg dabigatran etexilate mesylate) along with the following inactive ingredients: acacia, dimethicone, hydroxypropyl cellulose, hypromellose, talc, and tartaric acid. The capsule shell is composed of black edible ink, carrageenan, FD&C Blue No. 2 (150 mg and 110 mg capsules only), hypromellose, potassium chloride, and titanium dioxide.

12 CLINICAL PHARMACOLOGY

12.1 Mechanism of Action

Dabigatran and its acyl glucuronides are competitive, direct thrombin inhibitors. Because thrombin (serine protease) enables the conversion of fibrinogen into fibrin during the coagulation cascade, its inhibition prevents the development of a thrombus. Both free and clot-bound thrombin, and thrombin-induced platelet aggregation are inhibited by the active moieties.

12.2 Pharmacodynamics

At recommended therapeutic doses, dabigatran etexilate prolongs the coagulation markers such as aPTT, ECT, TT, and dTT. INR is relatively insensitive to the exposure to dabigatran and cannot be interpreted the same way as used for warfarin monitoring.

Adults

The aPTT test provides an approximation of PRADAXA's anticoagulant effect. The average time course for effects on aPTT, following approved dosing regimens in patients with various degrees of renal impairment is shown in Figure 2. The curves represent mean levels without confidence intervals; variations should be expected when measuring aPTT. While advice cannot be provided on the level of recovery of aPTT needed in any particular clinical setting, the curves can be used to estimate the time to get to a particular level of recovery, even when the time since the last dose of PRADAXA is not precisely known. In the RE-LY trial, the median (10th to 90th percentile) trough aPTT in patients receiving the 150 mg dose was 52 (40 to 76) seconds.

Figure 2 Average Time Course for Effects of Dabigatran on aPTT, Following Approved PRADAXA Dosing Regimens in Adult Patients with Various Degrees of Renal Impairment*

*Simulations based on PK data from a study in subjects with renal impairment and PK/aPTT relationships derived from the RE-LY study; aPTT prolongation in RE-LY was measured centrally in citrate plasma using PTT Reagent Roche Diagnostics GmbH, Mannheim, Germany. There may be quantitative differences between various established methods for aPTT assessment.

The degree of anticoagulant activity can also be assessed by the ecarin clotting time (ECT). This test is a more specific measure of the effect of dabigatran than activated partial thromboplastin time (aPTT). In the RE-LY trial, the median (10th to 90th percentile) trough ECT in patients receiving the 150 mg dose was 63 (44 to 103) seconds.

In orthopedic hip surgery patients, maximum aPTT response (Emax) to dabigatran and baseline aPTT were higher shortly after surgery than at later time points (e.g. ≥ 3 days after surgery).

Pediatrics

As in adults, there is a correlation between plasma dabigatran concentrations and the degree of its anticoagulant effect in pediatric patients with venous thromboembolism. The parameters dTT and ECT increased in direct linear proportion to the plasma concentration of dabigatran, whereas aPTT prolongation increases in a nonlinear fashion with dabigatran plasma concentrations.

Similar PK/PD relationships for aPTT, ECT, and dTT were observed across age groups of pediatric patients (ages 26 days to < 18 years) and between pediatric and adult patients with venous thromboembolism. This similarity in PK/PD relationship suggests that similar exposure-response relationship is expected for dabigatran etexilate treatment across the pediatric age groups and adult patients.

Cardiac Electrophysiology

No prolongation of the QTc interval was observed with dabigatran etexilate at doses up to 600 mg.

12.3 Pharmacokinetics

Dabigatran etexilate mesylate is absorbed as the dabigatran etexilate ester. The ester is then hydrolyzed, forming dabigatran, the active moiety. Dabigatran is metabolized to four different acyl glucuronides and both the glucuronides and dabigatran have similar pharmacological activity. Pharmacokinetics described here refer to the sum of dabigatran and its glucuronides. Dabigatran displays dose-proportional pharmacokinetics in healthy adult subjects and adult patients in the range of doses from 10 to 400 mg. Given twice daily, dabigatran's accumulation factor in adults and pediatrics is approximately two.

Absorption

The absolute bioavailability of dabigatran following oral administration of dabigatran etexilate is approximately 3% to 7%. Dabigatran etexilate is a substrate of the efflux transporter P-gp. After oral administration of dabigatran etexilate in healthy volunteers, Cmax occurs at 1-hour post-administration in the fasted state. Coadministration of PRADAXA with a high-fat meal delays the time to Cmax by approximately 2 hours but has no effect on the bioavailability of dabigatran; PRADAXA may be administered with or without food.

The oral bioavailability of dabigatran etexilate increases by 75% when the pellets are taken without the capsule shell compared to the intact capsule formulation based on a single-dose relative bioavailability study. PRADAXA Capsules should therefore not be broken, chewed, or opened before administration.

PRADAXA is available in capsules and oral pellets. The approved indications and intended age groups are not the same. Oral absorption of dabigatran etexilate is formulation-dependent. At steady-state, dabigatran etexilate oral pellets show 37% higher relative bioavailability in healthy adults compared to dabigatran etexilate capsules based on a multiple-dose relative bioavailability study. In addition, the relative bioavailability between the two dosage forms is age-dependent. The relative bioavailability observed in adults cannot be translated to pediatrics.

Distribution

Dabigatran is approximately 35% bound to human plasma proteins. The red blood cell to plasma partitioning of dabigatran measured as total radioactivity is less than 0.3. The volume of distribution of dabigatran is 50 to 70 L.

Elimination

Dabigatran is eliminated primarily in the urine. Renal clearance of dabigatran is 80% of total clearance after intravenous administration. After oral administration of radiolabeled dabigatran, 7% of radioactivity is recovered in urine and 86% in feces. The half-life of dabigatran in healthy adult subjects is 12 to 17 hours. Population pharmacokinetic simulation shows that the elimination half-life in pediatric patients is 12 to14 hours.

Metabolism

After oral administration, dabigatran etexilate is converted to dabigatran. The cleavage of the dabigatran etexilate by esterase-catalyzed hydrolysis to the active principal dabigatran is the predominant metabolic reaction. Dabigatran is not a substrate, inhibitor, or inducer of CYP450 enzymes. Dabigatran is subject to conjugation, forming pharmacologically active acyl glucuronides. Four positional isomers, 1-O, 2-O, 3-O, and 4-O-acylglucuronide exist, and each accounts for less than 10% of total dabigatran in plasma.

Specific Populations

Pediatric Patients

The pharmacokinetics of dabigatran was characterized in two clinical studies (DIVERSITY and Study 2) following multiple doses in pediatric patients from birth to less than 18 years old. In pediatric patients taking age- and weight-adjusted dosages of PRADAXA Capsules (aged 8-18 years), the observed geometric mean steady-state trough concentration was 97.9 ng/mL (63.7 to 151 ng/mL, 10th to 90th percentile) compared to the steady-state geometric mean trough concentration of 59.7 ng/mL (26.3 to 146 ng/mL, 10th to 90th percentile) observed in adult patients with DVT/PE.

Renal Impairment

An open, parallel-group, single-center study compared dabigatran pharmacokinetics in healthy adult subjects and adult patients with mild to moderate renal impairment receiving a single dose of PRADAXA Capsules 150 mg. Exposure to dabigatran increases with severity of renal function impairment (Table 10). Similar findings were observed in the RE-LY, RE-COVER and RE-NOVATE II trials.

Table 10 Impact of Renal Impairment on Dabigatran Pharmacokinetics
Renal Function | CrCl (mL/min) | Increase in AUC | Increase in Cmax | t1/2 (h)
Normal | ≥ 80 | 1× | 1× | 13
Mild | 50-80 | 1.5× | 1.1× | 15
Moderate | 30-50 | 3.2× | 1.7× | 18
Severe^+ | 15-30 | 6.3× | 2.1× | 27
^+Patients with severe renal impairment were not studied in RE-LY, RE-COVER and RE-NOVATE II. Dosing recommendations in subjects with severe renal impairment are based on pharmacokinetic modeling [see Dosage and Administration (2.2, 2.4) and Use in Specific Populations (8.6)].

Hepatic Impairment

Administration of PRADAXA Capsules in adult patients with moderate hepatic impairment (Child-Pugh B) showed a large inter-subject variability, but no evidence of a consistent change in exposure or pharmacodynamics.

Drug Interactions

A summary of the effect of coadministered drugs on dabigatran exposure in healthy adult subjects is shown in Figures 3.1 and 3.2.

In the orthopedic hip surgery patients, limited clinical data with P-gp inhibitors is available.

Figure 3.1

Effect of P-gp Inhibitor or Inducer (rifampicin) Drugs on Peak and Total Exposure to Dabigatran (Cmax and AUC). Shown are the Geometric Mean Ratios (Ratio) and 90% Confidence Interval (90% CI). The Perpetrator and Dabigatran Etexilate Dosage and Dosage Frequency are given as well as the Time of Perpetrator Dosage in Relation to Dabigatran Etexilate Dosage (Time Difference)

Figure 3.2

Effect of Non-P-gp Inhibitor or Inducer, Other Drugs, on Peak and Total Exposure to Dabigatran (Cmax and AUC). Shown are the Geometric Mean Ratios (Ratio) and 90% Confidence Interval (90% CI). The Perpetrator and Dabigatran Etexilate Dosage and Dosage Frequency are given as well as the Time of Perpetrator Dosage in Relation to Dabigatran Etexilate Dosage (Time Difference)

In RE-LY, dabigatran plasma samples were also collected. The concomitant use of proton pump inhibitors, H2 antagonists, and digoxin did not appreciably change the trough concentration of dabigatran.

Impact of Dabigatran on Other Drugs

In clinical studies exploring CYP3A4, CYP2C9, P-gp and other pathways, dabigatran did not meaningfully alter the pharmacokinetics of amiodarone, atorvastatin, clarithromycin, diclofenac, clopidogrel, digoxin, pantoprazole, or ranitidine.

13 NONCLINICAL TOXICOLOGY

13.1 Carcinogenesis, Mutagenesis, Impairment of Fertility

Dabigatran was not carcinogenic when administered by oral gavage to mice and rats for up to 2 years. The highest doses tested (200 mg/kg/day) in mice and rats were approximately 3.6 and 6 times, respectively, the human exposure at MRHD of 300 mg/day based on AUC comparisons.

Dabigatran was not mutagenic in in vitro tests, including bacterial reversion tests, mouse lymphoma assay and chromosomal aberration assay in human lymphocytes, and the in vivo micronucleus assay in rats.

In the rat fertility study with oral gavage doses of 15, 70, and 200 mg/kg, males were treated for 29 days prior to mating, during mating up to scheduled termination, and females were treated 15 days prior to mating through gestation Day 6. No adverse effects on male or female fertility were observed at 200 mg/kg or 9 to 12 times the human exposure at MRHD of 300 mg/day based on AUC comparisons. However, the number of implantations decreased in females receiving 70 mg/kg, or 3 times the human exposure at MRHD based on AUC comparisons.

14 CLINICAL STUDIES

14.1 Reduction of Risk of Stroke and Systemic Embolism in Non-valvular Atrial Fibrillation in Adult Patients

The clinical evidence for the efficacy of PRADAXA Capsules was derived from RE-LY (Randomized Evaluation of Long-term Anticoagulant Therapy), a multi-center, multi-national, randomized, parallel group trial comparing two blinded dosages of PRADAXA Capsules (110 mg twice daily and 150 mg twice daily) with open-label warfarin (dosed to target INR of 2 to 3) in patients with non-valvular, persistent, paroxysmal, or permanent atrial fibrillation and one or more of the following additional risk factors:

- Previous stroke, transient ischemic attack (TIA), or systemic embolism
- Left ventricular ejection fraction < 40%
- Symptomatic heart failure, ≥ New York Heart Association Class 2
- Age ≥ 75 years
- Age ≥ 65 years and one of the following: diabetes mellitus, coronary artery disease (CAD), or hypertension

The primary objective of this study was to determine if PRADAXA Capsules was non-inferior to warfarin in reducing the occurrence of the composite endpoint, stroke (ischemic and hemorrhagic) and systemic embolism. The study was designed to ensure that PRADAXA Capsules preserved more than 50% of warfarin's effect as established by previous randomized, placebo-controlled trials of warfarin in atrial fibrillation. Statistical superiority was also analyzed.

A total of 18,113 patients were randomized and followed for a median of 2 years. The patients' mean age was 71.5 years and the mean CHADS2 score was 2.1. The patient population was 64% male, 70% Caucasian, 16% Asian, and 1% black. Twenty percent of patients had a history of a stroke or TIA and 50% were vitamin K antagonist (VKA) naïve, defined as less than 2 months total lifetime exposure to a VKA. Thirty-two percent of the population had never been exposed to a VKA. Concomitant diseases of patients in this trial included hypertension 79%, diabetes 23%, and CAD 28%. At baseline, 40% of patients were on aspirin and 6% were on clopidogrel. For patients randomized to warfarin, the mean percentage of time in therapeutic range (INR 2 to 3) was 64%.

Relative to warfarin and to PRADAXA Capsules 110 mg twice daily, PRADAXA Capsules 150 mg twice daily significantly reduced the primary composite endpoint of stroke and systemic embolism (see Table 11 and Figure 4).

Table 11 First Occurrence of Stroke or Systemic Embolism in the RE-LY Study*
 | PRADAXA Capsules 150 mg twice daily | PRADAXA Capsules 110 mg twice daily | Warfarin
Patients randomized | 6,076 | 6,015 | 6,022
Patients (% per yr) with events | 135 (1.12%) | 183 (1.54%) | 203 (1.72%)
Hazard ratio vs warfarin (95% CI) | 0.65 (0.52, 0.81) | 0.89 (0.73, 1.09)
P-value for superiority | 0.0001 | 0.27
Hazard ratio vs PRADAXA 110 mg (95% CI) | 0.72 (0.58, 0.91)
P-value for superiority | 0.005
* Randomized ITT

Figure 4 Kaplan-Meier Curve Estimate of Time to First Stroke or Systemic Embolism

The contributions of the components of the composite endpoint, including stroke by subtype, are shown in Table 12. The treatment effect was primarily a reduction in stroke. PRADAXA Capsules 150 mg twice daily was superior in reducing ischemic and hemorrhagic strokes relative to warfarin.

Table 12 Strokes and Systemic Embolism in the RE-LY Study
 | PRADAXA Capsules 150 mg twice daily | Warfarin | Hazard ratio vs warfarin (95% CI)
Patients randomized | 6,076 | 6,022
Stroke | 123 | 187 | 0.64 (0.51, 0.81)
Ischemic stroke | 104 | 134 | 0.76 (0.59, 0.98)
Hemorrhagic stroke | 12 | 45 | 0.26 (0.14, 0.49)
Systemic embolism | 13 | 21 | 0.61 (0.30, 1.21)

In the RE-LY trial, the rate of all-cause mortality was lower on PRADAXA Capsules 150 mg than on warfarin (3.6% per year versus 4.1% per year). The rate of vascular death was lower on PRADAXA Capsules 150 mg compared to warfarin (2.3% per year versus 2.7% per year). Non-vascular death rates were similar in the treatment arms.

The efficacy of PRADAXA Capsules 150 mg twice daily was generally consistent across major subgroups (see Figure 5).

Figure 5 Stroke and Systemic Embolism Hazard Ratios by Baseline Characteristics*

* Randomized ITT
Note: The figure above presents effects in various subgroups all of which are baseline characteristics and all of which were pre-specified. The 95% confidence limits that are shown do not take into account how many comparisons were made, nor do they reflect the effect of a particular factor after adjustment for all other factors. Apparent homogeneity or heterogeneity among groups should not be over-interpreted.

In RE-LY, a higher rate of clinical myocardial infarction was reported in patients who received PRADAXA Capsules (0.7 per 100 patient-years for 150 mg dose) than in those who received warfarin (0.6).

14.2 Treatment and Reduction in the Risk of Recurrence of Deep Venous Thrombosis and Pulmonary Embolism in Adult Patients

In the randomized, parallel group, double-blind trials, RE-COVER and RE-COVER II, patients with deep vein thrombosis and pulmonary embolism received PRADAXA Capsules 150 mg twice daily or warfarin (dosed to target INR of 2 to 3) following initial treatment with an approved parenteral anticoagulant for 5 to 10 days.

In RE-COVER, the median treatment duration during the oral only treatment period was 174 days. A total of 2,539 patients (30.9% patients with symptomatic PE with or without DVT and 68.9% with symptomatic DVT only) were treated with a mean age of 54.7 years. The patient population was 58.4% male, 94.8% white, 2.6% Asian, and 2.6% black. The concomitant diseases of patients in this trial included hypertension (35.9%), diabetes mellitus (8.3%), coronary artery disease (6.5%), active cancer (4.8%), and gastric or duodenal ulcer (4.4%). Concomitant medications included agents acting on renin-angiotensin system (25.2%), vasodilators (28.4%), serum lipid-reducing agents (18.2%), NSAIDs (21%), beta-blockers (14.8%), calcium channel blockers (8.5%), ASA (8.6%), and platelet inhibitors excluding ASA (0.6%). Patients randomized to warfarin had a mean percentage of time in the INR target range of 2.0 to 3.0 of 60% in RE-COVER study.

In RE-COVER II, the median treatment duration during the oral only treatment period was 174 days. A total of 2,568 patients (31.8% patients with symptomatic PE with or without DVT and 68.1% with symptomatic DVT only) were treated with a mean age of 54.9 years. The patient population was 60.6% male, 77.6% white, 20.9% Asian, and 1.5% black. The concomitant diseases of patients in this trial included hypertension (35.1%), diabetes mellitus (9.8%), coronary artery disease (7.1%), active cancer (3.9%), and gastric or duodenal ulcer (3.8%). Concomitant medications included agents acting on renin-angiotensin system (24.2%), vasodilators (28.6%), serum lipid-reducing agents (20.0%), NSAIDs (22.3%), beta-blockers (14.8%), calcium channel blockers (10.8%), ASA (9.8%), and platelet inhibitors excluding ASA (0.8%). Patients randomized to warfarin had a mean percentage of time in the INR target range of 2.0 to 3.0 of 57% in RE-COVER II study.

In studies RE-COVER and RE-COVER II, the protocol specified non-inferiority margin (2.75) for the hazard ratio was derived based on the upper limit of the 95% confidence interval of the historical warfarin effect. PRADAXA Capsules was demonstrated to be non-inferior to warfarin (dosed to target INR of 2 to 3) (Table 13) based on the primary composite endpoint (fatal PE or symptomatic non-fatal PE and/or DVT) and retains at least 66.9% (RE-COVER) and 63.9% (RE-COVER II) of the historical warfarin effect, respectively.

Table 13 Primary Efficacy Endpoint for RE-COVER and RE-COVER II – Modified ITTa Population
 | PRADAXA Capsules 150 mg twice daily N (%) | Warfarin N (%) | Hazard ratio vs warfarin (95% CI)
RE-COVER | N=1,274 | N=1,265
Primary Composite Endpointb | 34 (2.7) | 32 (2.5) | 1.05 (0.65, 1.70)
Fatal PEc | 1 (0.1) | 3 (0.2)
Symptomatic non-fatal PEc | 16 (1.3) | 8 (0.6)
Symptomatic recurrent DVTc | 17 (1.3) | 23 (1.8)
RE-COVER II | N=1,279 | N=1,289
Primary Composite Endpointb | 34 (2.7) | 30 (2.3) | 1.13 (0.69, 1.85)
Fatal PEc | 3 (0.2) | 0
Symptomatic non-fatal PEc | 9 (0.7) | 15 (1.2)
Symptomatic recurrent DVTc | 30 (2.3) | 17 (1.3)
aModified ITT analyses population consists of all randomized patients who received at least one dose of study medication.
bNumber of patients with one or more event.
cNumber of events. For patients with multiple events each event is counted independently.

In the randomized, parallel-group, double-blind, pivotal trial, RE-MEDY, patients received PRADAXA Capsules 150 mg twice daily or warfarin (dosed to target INR of 2 to 3) following 3 to 12 months of treatment with anticoagulation therapy for an acute VTE. The median treatment duration during the treatment period was 534 days. A total of 2,856 patients were treated with a mean age of 54.6 years. The patient population was 61% male, and 90.1% white, 7.9% Asian and 2.0% black. The concomitant diseases of patients in this trial included hypertension (38.6%), diabetes mellitus (9.0%), coronary artery disease (7.2%), active cancer (4.2%), and gastric or duodenal ulcer (3.8%). Concomitant medications included agents acting on renin-angiotensin system (27.9%), vasodilators (26.7%), serum lipid reducing agents (20.6%), NSAIDs (18.3%), beta-blockers (16.3%), calcium channel blockers (11.1%), aspirin (7.7%), and platelet inhibitors excluding ASA (0.9%). Patients randomized to warfarin had a mean percentage of time in the INR target range of 2.0 to 3.0 of 62% in the study.

In study RE-MEDY, the protocol specified non-inferiority margin (2.85) for the hazard ratio was derived based on the point estimate of the historical warfarin effect. PRADAXA Capsules was demonstrated to be non-inferior to warfarin (dosed to target INR of 2 to 3) (Table 14) based on the primary composite endpoint (fatal PE or symptomatic non-fatal PE and/or DVT) and retains at least 63.0% of the historical warfarin effect. If the non-inferiority margin was derived based on the 50% retention of the upper limit of the 95% confidence interval, PRADAXA Capsules was demonstrated to retain at least 33.4% of the historical warfarin effect based on the composite primary endpoint.

Table 14 Primary Efficacy Endpoint for RE-MEDY – Modified ITTa Population
 | PRADAXA Capsules 150 mg twice daily N=1,430 N (%) | Warfarin N=1,426 N (%) | Hazard ratio vs warfarin (95% CI)
Primary Composite Endpointb | 26 (1.8) | 18 (1.3) | 1.44 (0.78, 2.64)
Fatal PEc | 1 (0.07) | 1 (0.07)
Symptomatic non-fatal PEc | 10 (0.7) | 5 (0.4)
Symptomatic recurrent DVTc | 17 (1.2) | 13 (0.9)
aModified ITT analyses population consists of all randomized patients who received at least one dose of study medication.
bNumber of patients with one or more event.
cNumber of events. For patients with multiple events each event is counted independently.

In a randomized, parallel-group, double-blind, pivotal trial, RE-SONATE, patients received PRADAXA Capsules 150 mg twice daily or placebo following 6 to 18 months of treatment with anticoagulation therapy for an acute VTE. The median treatment duration was 182 days. A total of 1,343 patients were treated with a mean age of 55.8 years. The patient population was 55.5% male, 89.0% white, 9.3% Asian, and 1.7% black. The concomitant diseases of patients in this trial included hypertension (38.8%), diabetes mellitus (8.0%), coronary artery disease (6.0%), history of cancer (6.0%), gastric or duodenal ulcer (4.5%), and heart failure (4.6%). Concomitant medications included agents acting on renin-angiotensin system (28.7%), vasodilators (19.4%), beta-blockers (18.5%), serum lipid reducing agents (17.9%), NSAIDs (12.1%), calcium channel blockers (8.9%), aspirin (8.3%), and platelet inhibitors excluding ASA (0.7%). Based on the outcome of the primary composite endpoint (fatal PE, unexplained death, or symptomatic non-fatal PE and/or DVT), PRADAXA was superior to placebo (Table 15).

Table 15 Primary Efficacy Endpoint for RE-SONATE – Modified ITTa Population
 | PRADAXA Capsules 150 mg twice daily N=681 N (%) | Placebo N=662 N (%) | Hazard ratio vs placebo (95% CI)
Primary Composite Endpointb | 3 (0.4) | 37 (5.6) | 0.08 (0.02, 0.25) p-value <0.0001
Fatal PE and unexplained deathc | 0 | 2 (0.3)
Symptomatic non-fatal PEc | 1 (0.1) | 14 (2.1)
Symptomatic recurrent DVTc | 2 (0.3) | 23 (3.5)
aModified ITT analyses population consists of all randomized patients who received at least one dose of study medication.
bNumber of patients with one or more events.
cNumber of events. For patients with multiple events each event is counted independently.

14.3 Prophylaxis of Deep Vein Thrombosis and Pulmonary Embolism in Adult Patients Following Hip Replacement Surgery

In the randomized, parallel-group, double-blind, non-inferiority trials, RE-NOVATE and RE-NOVATE II patients received PRADAXA Capsules 75 mg orally 1-4 hours after surgery followed by 150 mg daily (RE-NOVATE), PRADAXA Capsules 110 mg orally 1-4 hours after surgery followed by 220 mg daily (RE-NOVATE and RE-NOVATE II) or subcutaneous enoxaparin 40 mg once daily initiated the evening before surgery (RE-NOVATE and RE-NOVATE II) for the prophylaxis of deep vein thrombosis and pulmonary embolism in patients who have undergone hip replacement surgery.

Overall, in RE-NOVATE and RE-NOVATE II, the median treatment duration was 33 days for PRADAXA Capsules and 33 days for enoxaparin. A total of 5,428 patients were treated with a mean age of 63.2 years. The patient population was 45.3% male, 96.1% white, 3.6% Asian, and 0.4 % black. The concomitant diseases of patients in these trials included hypertension (46.1%), venous insufficiency (15.4%), coronary artery disease (8.2%), diabetes mellitus (7.9%), reduced renal function (5.3%), heart failure (3.4%), gastric or duodenal ulcer (3.0%), VTE (2.7%), and malignancy (0.1%). Concomitant medications included cardiac therapy (69.7%), NSAIDs (68%), vasoprotectives (29.7%), agents acting on renin-angiotensin system (29.1%), beta-blockers (21.5%), diuretics (20.8%), lipid modifying agents (18.2%), any antithrombin/anticoagulant (16.0%), calcium channel blockers (13.6%), low molecular weight heparin (7.8%), aspirin (7.0%), platelet inhibitors excluding ASA (6.9%), other antihypertensives (6.7%), and peripheral vasodilators (2.6%).

For efficacy evaluation all patients were to have bilateral venography of the lower extremities at 3 days after last dose of study drug unless an endpoint event had occurred earlier in the study. In the primary efficacy analysis, PRADAXA Capsules 110 mg orally 1-4 hours after surgery followed by 220 mg daily was non-inferior to enoxaparin 40 mg once daily in a composite endpoint of confirmed VTE (proximal or distal DVT on venogram, confirmed symptomatic DVT, or confirmed PE) and all cause death during the treatment period (Tables 16 and 17). In the studies 2628 (76.5%) patients in RE-NOVATE and 1572 (78.9%) patients in RE-NOVATE II had evaluable venograms at study completion.

Table 16 Primary Efficacy Endpoint for RE-NOVATE
 | PRADAXA Capsules 220 mg N (%) | Enoxaparin N (%)
Number of Patientsa | N=880 | N= 897
Primary Composite Endpoint | 53 (6.0) | 60 (6.7)
Risk difference (%) vs enoxaparin (95% CI) | -0.7 (-2.9, 1.6)
Number of Patients | N=909 | N=917
Composite endpoint of major VTEb and VTE related mortality | 28 (3.1) | 36 (3.9)
Number of Patients | N=905 | N=914
Proximal DVT | 23 (2.5) | 33 (3.6)
Number of Patients | N=874 | N=894
Total DVT | 46 (5.3) | 57 (6.4)
Number of Patients | N=1,137 | N=1,142
Symptomatic DVT | 6 (0.5) | 1 (0.1)
PE | 5 (0.4) | 3 (0.3)
Death | 3 (0.3) | 0
aFull Analysis Set (FAS): The FAS included all randomized patients who received at least one subcutaneous injection or one oral dose of study medication, underwent surgery and subjects for whom the presence or absence of an efficacy outcome at the end of the study was known, i.e., an evaluable negative venogram for both distal and proximal DVT in both legs or any of the following: positive venography in one or both legs, or confirmed symptomatic DVT, PE, or death during the treatment period.
bVTE is defined as proximal DVT and PE

Table 17 Primary Efficacy Endpoint for RE-NOVATE II
 | PRADAXA Capsules 220 mg N (%) | Enoxaparin N (%)
Number of Patientsa | N=792 | N= 786
Primary Composite Endpoint | 61 (7.7) | 69 (8.8)
Risk difference (%) vs enoxaparin (95% CI) | -1.1 (-3.8, 1.6)
Number of Patients | N=805 | N=795
Composite endpoint of major VTEb and VTE related mortality | 18 (2.2) | 33 (4.2)
Number of Patients | N=804 | N=793
Proximal DVT | 17 (2.1) | 31 (3.9)
Number of Patients | N=791 | N=784
Total DVT | 60 (7.6) | 67 (8.5)
Number of Patients | N=1,001 | N=992
Symptomatic DVT | 0 | 4 (0.4)
PE | 1 (0.1) | 2 (0.2)
Death | 0 | 1 (0.1)
aFull Analysis Set (FAS): The FAS included all randomized patients who received at least one subcutaneous injection or one oral dose of study medication, underwent surgery and subjects for whom the presence or absence of an efficacy outcome at the end of the study was known, i.e., an evaluable negative venogram for both distal and proximal DVT in both legs or any of the following: positive venography in one or both legs, or confirmed symptomatic DVT, PE, or death during the treatment period.
bVTE is defined as proximal DVT and PE

14.4 Treatment of VTE in Pediatric Patients

The DIVERSITY study was conducted to demonstrate the efficacy and safety of PRADAXA compared to standard of care (SOC) for the treatment of venous thromboembolism (VTE) in pediatric patients from birth to less than 18 years of age. The study was designed as an open-label, randomized, parallel-group, non-inferiority study. Patients enrolled were randomized according to a 2:1 scheme to either an age-appropriate formulation (capsules, oral pellets, or oral solution) of PRADAXA (doses adjusted for age and weight) after at least 5 days and no longer than 21 days of treatment with a parenteral anticoagulant, or to SOC comprised of low molecular weight heparins (LMWH) or vitamin K antagonists (VKA) or fondaparinux. For patients on PRADAXA, drug concentration was determined prior to the 7th dose and a single titration was permitted to achieve drug target levels of 50-250 ng/mL. Inability to achieve target, after one up-titration, resulted in premature termination of study drug in 12 patients (6.8%).

The median treatment duration during the treatment period was 85 days. In total, 267 patients entered the study (leading index VTE was 64% deep vein thrombosis, 10% cerebral venous thrombosis or sinus thrombosis, and 9.0% pulmonary embolism), with 18% of patients having a central line-associated thrombosis. The patient population was 49.8% male, 91.8% white, 4.9% Asian, and 1.5% black; 168 patients were 12 to < 18 years old, 64 patients 2 to < 12 years, and 35 patients were younger than 2 years. The concomitant VTE-related risk factors of patients in this trial among study arms were as follows: inherited thrombophilia disorder (PRADAXA: 20%, SOC: 22%), congenital heart disease (PRADAXA: 12%, SOC: 30%), heart failure (PRADAXA: 3%, SOC: 18%), history of cancer (PRADAXA: 10%, SOC: 1%), CVL insertion (PRADAXA: 23%, SOC: 27%), immobility (PRADAXA: 13%, SOC: 10%) and significant infection (PRADAXA: 15%, SOC: 13%). The number of patients taking concomitant medications with hemostatic effects were similar in both treatment groups (PRADAXA: 15%, SOC: 16%).

The efficacy of PRADAXA was established based on a composite endpoint of patients with complete thrombus resolution, freedom from recurrent venous thromboembolic event, and freedom from mortality related to venous thromboembolic event (composite primary endpoint). Of the 267 randomized patients, 81 patients (45.8%) in the PRADAXA group and 38 patients (42.2%) in the SOC group met the criteria for the composite primary endpoint. The corresponding rate difference and 95% CI was -0.038 (-0.161, 0.086) and thus demonstrated non-inferiority of PRADAXA to SOC, since the upper bound of the 95% CI was lower than the predefined non-inferiority margin of 20% (see Table 18).

Table 18: Efficacy Results [ITT population] DIVERSITY Study
 | PRADAXA |  | Standard of Care
Number of patients randomized (%) | 177 (100.0) |  | 90 (100.0)
Complete thrombus resolution | 81 | (45.8) | 38 | (42.2)
Freedom from recurrent VTE | 170 | (96.0) | 83 | (92.2)
Freedom from mortality related to VTE | 177 | (100.0) | 89 | (98.9)
Composite endpoint met | 81 | (45.8) | 38 | (42.2)
Difference in rate (95% CI)^1 | -0.038 (-0.161, 0.086)
p-value for non-inferiority | < 0.0001
p-value for superiority | 0.2739
^1 Mantel-Haenszel weighted difference with age group as stratification factor

Subgroup analyses showed that there were no outliers in the treatment effect for the subgroups by age, sex, region, and presence of certain risk factors (central venous line, congenital heart disease, malignant disease). For the 3 different age strata, the proportions of patients that met the efficacy endpoint in the PRADAXA and SOC groups, respectively, were 13/22 (59.1%) and 7/13 (53.8%) for patients from birth to < 2 years [Rate Difference -0.052; (95%CI: -0.393, 0.288)], 21/43 (48.8%) and 12/21 (57.1%) for patients aged 2 to < 12 years [Rate Difference 0.083; (95%CI: -0.176, 0.342)], and 47/112 (42.0%) and 19/56 (33.9%) for patients aged 12 to < 18 years [Rate Difference -0.080; (95%CI: -0.234, 0.074)].

14.5 Reduction in the Risk of Recurrence of VTE in Pediatric Patients

Study 2 was an open-label, single-arm safety study to assess the safety of PRADAXA for the prevention of recurrent VTE in pediatric patients from birth to < 18 years. Patients who required further anticoagulation due to the presence of a clinical risk factor after completing the initial treatment for confirmed VTE (for at least 3 months) or after completing the DIVERSITY study were included in the study. Eligible patients received age- and weight adjusted dosages of an age-appropriate formulation (capsules or oral pellets) of PRADAXA until the clinical risk factor resolved, or up to a maximum of 12 months. The primary endpoints of the study included the recurrence of VTE, major and minor bleeding events, and mortality (overall and related to thrombotic or thromboembolic events) at 6 and 12 months.

Of the 214 patients in the study, 162 patients were 12 to < 18 years old, 43 patients were 2 to < 12 years old, and 9 patients were aged 6 months to < 2 years old.

The overall probability of being free from recurrence of VTE during the on-treatment period was 0.990 (95% CI: 0.960, 0.997) at 3 months, 0.984 (95% CI: 0.950, 0.995) at 6 months, and 0.984 (95% CI: 0.950, 0.995) at 12 months. The probability of being free from bleeding events during the on-treatment period was 0.849 (95% CI: 0.792, 0.891) at 3 months, 0.785 (95% CI: 0.718, 0.838) at 6 months, and 0.723 (95% CI: 0.645, 0.787) at 12 months. No on-treatment deaths occurred.

16 HOW SUPPLIED/STORAGE AND HANDLING

PRADAXA 75 mg capsules have a white opaque cap imprinted with the Boehringer Ingelheim company symbol and a white opaque body imprinted with "R75". The color of the imprinting is black. The capsules are supplied in the packages listed:

- NDC 0597-0355-09 Unit of use bottle of 60 capsules
- NDC 0597-0355-56 Blister package containing 60 capsules (10 × 6 capsule blister cards)

PRADAXA 110 mg capsules have a light blue opaque cap imprinted with the Boehringer Ingelheim company symbol and a light blue opaque body imprinted with "R110". The color of the imprinting is black. The capsules are supplied in the packages listed:

- NDC 0597-0108-54 Unit of use bottle of 60 capsules
- NDC 0597-0108-60 Blister package containing 60 capsules (10 × 6 capsule blister cards)

PRADAXA 150 mg capsules have a light blue opaque cap imprinted with the Boehringer Ingelheim company symbol and a white opaque body imprinted with "R150". The color of the imprinting is black. The capsules are supplied in the packages listed:

- NDC 0597-0360-55 Unit of use bottle of 60 capsules
- NDC 0597-0360-82 Blister package containing 60 capsules (10 × 6 capsule blister cards)

STORAGE AND HANDLING

Bottles

Store at 20°C to 25°C (68°F to 77°F); excursions permitted to 15°C to 30°C (59°F to 86°F) [see USP Controlled Room Temperature]. Once opened, the product must be used within 4 months. Keep the bottle tightly closed. Store in the original package to protect from moisture.

STORAGE AND HANDLING

Blisters

Store at 20°C to 25°C (68°F to 77°F); excursions permitted to 15°C to 30°C (59°F to 86°F) [see USP Controlled Room Temperature]. Store in the original package to protect from moisture.

17 PATIENT COUNSELING INFORMATION

Advise the patient or caregiver to read the FDA-approved patient labeling (Medication Guide).

Instructions for Patients

- Tell patients to take PRADAXA Capsules exactly as prescribed.
- Remind patients not to discontinue PRADAXA Capsules without talking to the healthcare provider who prescribed it.
- Keep PRADAXA Capsules in the original bottle to protect from moisture. Do not put PRADAXA Capsules in pill boxes or pill organizers.
- When more than one bottle is dispensed to the patient, instruct them to open only one bottle at a time.
- Instruct patient to remove only one capsule from the opened bottle at the time of use. The bottle should be immediately and tightly closed.
- Advise patients not to chew or break the capsules before swallowing them and not to open the capsules and take the pellets alone.
- Advise patients that the capsule should be taken with a full glass of water.

[see Boxed Warning, Dosage and Administration (2.5)]

Bleeding

Inform patients that they may bleed more easily, may bleed longer, and should call their healthcare provider for any signs or symptoms of bleeding [see Warnings and Precautions (5.2)].

Instruct patients to seek emergency care right away if they have any of the following, which may be a sign or symptom of serious bleeding:

- Unusual bruising (bruises that appear without known cause or that get bigger)
- Pink or brown urine
- Red or black, tarry stools
- Coughing up blood
- Vomiting blood, or vomit that looks like coffee grounds

Instruct patients to call their healthcare provider or to get prompt medical attention if they experience any signs or symptoms of bleeding:

- Pain, swelling or discomfort in a joint
- Headaches, dizziness, or weakness
- Reoccurring nose bleeds
- Unusual bleeding from gums
- Bleeding from a cut that takes a long time to stop
- Menstrual bleeding or vaginal bleeding that is heavier than normal

If patients have had neuraxial anesthesia or spinal puncture, and particularly, if they are taking concomitant NSAIDs or platelet inhibitors, advise patients to watch for signs and symptoms of spinal or epidural hematoma, such as back pain, tingling, numbness (especially in the lower limbs), muscle weakness, and stool or urine incontinence. If any of these symptoms occur, advise the patient to contact his or her physician immediately [see Boxed Warning].

Gastrointestinal Adverse Reactions

Instruct patients to call their healthcare provider if they experience any signs or symptoms of dyspepsia or gastritis:

- Dyspepsia (upset stomach), burning, or nausea
- Abdominal pain or discomfort
- Epigastric discomfort, GERD (gastric indigestion)

[see Adverse Reactions (6.1)]

Invasive or Surgical Procedures

Instruct patients to inform their healthcare provider that they are taking PRADAXA before any invasive procedure (including dental procedures) is scheduled [see Dosage and Administration (2.8)].

Concomitant Medications

Ask patients to list all prescription medications, over-the-counter medications, or dietary supplements they are taking or plan to take so their healthcare provider knows about other treatments that may affect bleeding risk (e.g., aspirin or NSAIDs) or dabigatran exposure (e.g., dronedarone or systemic ketoconazole) [see Warnings and Precautions (5.2, 5.5)].

Prosthetic Heart Valves

Instruct patients to inform their healthcare provider if they will have or have had surgery to place a prosthetic heart valve [see Warnings and Precautions (5.4)].

Allergic Reactions

Advise adult patients and caregivers that some adults taking PRADAXA have developed symptoms of an allergic reaction. Advise adult patients or caregivers to inform their healthcare provider if they or their child develop symptoms of an allergic reaction, such as hives, rash, or itching. Advise adult patients or caregivers to seek emergency medical attention if they or their child develop chest pain or tightness, swelling of the face or tongue, trouble breathing or wheezing, or feeling dizzy or faint.

Pregnancy

Advise patients to inform their healthcare provider immediately if they become pregnant or intend to become pregnant during treatment with PRADAXA Capsules [see Use in Specific Populations (8.1)].

Lactation

Advise patients not to breastfeed if they are taking PRADAXA Capsules [see Use in Specific Populations (8.2)].

Distributed by:
Boehringer Ingelheim Pharmaceuticals, Inc.
Ridgefield, CT 06877 USA

PRADAXA is a registered trademark of and used under license from Boehringer Ingelheim International GmbH.

Copyright © 2025 Boehringer Ingelheim Pharmaceuticals, Inc.
ALL RIGHTS RESERVED

COL8774FF232025

MEDICATION GUIDE
PRADAXA (pra dax a)
(dabigatran etexilate)
Capsules

This Medication Guide is for PRADAXA Capsules. If your healthcare provider prescribes PRADAXA Oral Pellets for you, read the Medication Guide that comes with your medicine.
Read this Medication Guide before you start taking PRADAXA Capsules and each time you get a refill. There may be new information. This Medication Guide does not take the place of talking with your healthcare provider about your medical condition or your treatment.

What is the most important information I should know about PRADAXA?

- People with atrial fibrillation (a type of irregular heartbeat) are at an increased risk of forming a blood clot in the heart, which can travel to the brain, causing a stroke, or to other parts of the body. PRADAXA lowers your chance of having a stroke by helping to prevent clots from forming. If you stop taking PRADAXA, you may have increased risk of forming a clot in your blood.
  Do not stop taking PRADAXA Capsules without talking to the healthcare provider who prescribes it for you. Stopping PRADAXA increases your risk of having a stroke.
  PRADAXA may need to be stopped, if possible, before surgery or a medical or dental procedure. Ask the healthcare provider who prescribed PRADAXA for you when you should stop taking it. Your healthcare provider will tell you when you may start taking PRADAXA again after your surgery or procedure. If you have to stop taking PRADAXA, your healthcare provider may prescribe another medicine to help prevent a blood clot from forming.
- PRADAXA can cause bleeding which can be serious, and sometimes lead to death. This is because PRADAXA is a blood thinner medicine that lowers the chance of blood clots forming in your body.
- You may have a higher risk of bleeding if you take PRADAXA and:
  - are over 75 years old
  - have kidney problems
  - have stomach or intestine bleeding that is recent or keeps coming back, or you have a stomach ulcer
  - take other medicines that increase your risk of bleeding, including:
    - aspirin or aspirin-containing products
    - long-term (chronic) use of non-steroidal anti-inflammatory drugs (NSAIDs)
    - a medicine that contains warfarin sodium
    - a medicine that contains heparin
    - a medicine that contains clopidogrel bisulfate
    - a medicine that contains prasugrel
  - have certain kidney problems and also take a medicine that contains dronedarone or ketoconazole tablets.
    Tell your healthcare provider if you take any of these medicines. Ask your healthcare provider or pharmacist if you are not sure if your medicine is one listed above.
- PRADAXA can increase your risk of bleeding because it lessens the ability of your blood to clot. During treatment with PRADAXA:
  - you may bruise more easily
  - it may take longer for any bleeding to stop
  Call your healthcare provider or get medical help right away if you have any of these signs or symptoms of bleeding:
  - unexpected bleeding or bleeding that lasts a long time, such as:
    - unusual bleeding from the gums
    - nose bleeds that happen often
    - menstrual bleeding or vaginal bleeding that is heavier than normal
  - bleeding that is severe or you cannot control
  - pink or brown urine
  - red or black stools (looks like tar)
  - bruises that happen without a known cause or get larger
  - cough up blood or blood clots
  - vomit blood or your vomit looks like "coffee grounds"
  - unexpected pain, swelling, or joint pain
  - headaches, feeling dizzy or weak
  Take PRADAXA Capsules exactly as prescribed. Do not stop taking PRADAXA Capsules without first talking to the healthcare provider who prescribes it for you. Stopping PRADAXA may increase your risk of a stroke.
- Spinal or epidural blood clots (hematoma). People who take a blood thinner medicine (anticoagulant) like PRADAXA, and have medicine injected into their spinal and epidural area, or have a spinal puncture have a risk of forming a blood clot that can cause long-term or permanent loss of the ability to move (paralysis). Your risk of developing a spinal or epidural blood clot is higher if:
  - a thin tube called an epidural catheter is placed in your back to give you certain medicine
  - you take NSAIDs or a medicine to prevent blood from clotting
  - you have a history of difficult or repeated epidural or spinal punctures
  - you have a history of problems with your spine or have had surgery on your spine
  If you take PRADAXA and receive spinal anesthesia or have a spinal puncture, your healthcare provider should watch you closely for symptoms of spinal or epidural blood clots. Tell your healthcare provider right away if you have back pain, tingling, numbness, muscle weakness (especially in your legs and feet), loss of control of the bowels or bladder (incontinence).

See "What are the possible side effects of PRADAXA?" for more information about side effects.

What is PRADAXA?
PRADAXA is a prescription medicine that is used to:

- in adults:
  - reduce the risk of stroke and blood clots in adults who have a medical condition called atrial fibrillation that is not caused by a heart valve problem. With atrial fibrillation, part of the heart does not beat the way it should. This can lead to blood clots forming and increase your risk of a stroke.
  - treat blood clots in the veins of your legs (deep vein thrombosis) and lungs (pulmonary embolism) after you have been treated with an injectable medicine to treat your blood clots for 5 to 10 days.
  - reduce your risk of blood clots from happening again in the veins of your legs (deep vein thrombosis) and lungs (pulmonary embolism) after you have received treatment for blood clots.
  - help prevent blood clots in your legs (venous thrombosis) and lungs (pulmonary embolism) after you have just had hip replacement surgery.
- in children:
  - treat blood clots in children 8 years to less than 18 years of age who have received an injectable medicine to treat their blood clots for at least 5 days.
  - reduce the risk of blood clots from happening again in children 8 years to less than 18 years of age who have received treatment for blood clots.

It is not known if PRADAXA Capsules are safe and effective in children with atrial fibrillation not caused by a heart valve problem, or in children who have undergone hip replacement surgery.

Do not take PRADAXA if you:

- currently have certain types of abnormal bleeding. Talk to your healthcare provider before taking PRADAXA if you currently have unusual bleeding.
- have had a serious allergic reaction to any of the ingredients in PRADAXA. See the end of this Medication Guide for a complete list of ingredients in PRADAXA. Ask your healthcare provider if you are not sure.
- have ever had or plan to have a valve in your heart replaced with a mechanical (artificial) prosthetic heart valve

Before taking PRADAXA, tell your healthcare provider about all of your medical conditions, including if you:

- have kidney problems
- have ever had bleeding problems
- have ever had stomach ulcers
- have antiphospholipid syndrome (APS)
- are pregnant or plan to become pregnant. It is not known if PRADAXA will harm your unborn baby. Tell your healthcare provider right away if you become pregnant during treatment with PRADAXA.
  Females who are able to become pregnant: Talk with your healthcare provider about pregnancy planning during treatment with PRADAXA. Talk with your healthcare provider about your risk for severe uterine bleeding if you are treated with blood thinner medicines, including PRADAXA.
- are breastfeeding or plan to breastfeed. It is not known if PRADAXA passes into your breast milk. You should not breastfeed during treatment with PRADAXA Capsules. Talk to your healthcare provider about the best way to feed your baby during treatment with PRADAXA Capsules.

Tell all of your healthcare providers and dentists that you are taking PRADAXA. They should talk to the healthcare provider who prescribed PRADAXA for you before you have any surgery or a medical or dental procedure.
Tell your healthcare provider about all the medicines you take, including prescription and over-the-counter medicines, vitamins, and herbal supplements.
Some of your other medicines may affect the way PRADAXA works. Certain medicines may increase your risk of bleeding. See "What is the most important information I should know about PRADAXA?"
Especially tell your healthcare provider if you take a medicine that contains rifampin.
Know the medicines you take. Keep a list of them and show it to your healthcare provider and pharmacist when you get a new medicine.

How should I take PRADAXA Capsules?

- PRADAXA comes as capsules and oral pellets. If you have a child who is older than 8 years of age and who is prescribed PRADAXA, your healthcare provider will prescribe the type of PRADAXA that is right for your child.
- Your healthcare provider will decide how long you should take PRADAXA. Do not stop taking PRADAXA Capsules without first talking with your healthcare provider. Stopping PRADAXA may increase your risk of having a stroke or forming blood clots.
- Take PRADAXA Capsules exactly as prescribed by your healthcare provider.
- If PRADAXA is prescribed for your child, your healthcare provider will determine the correct dose of PRADAXA Capsules for your child based on their weight. Your healthcare provider may increase or decrease your child's dose as they grow during treatment and as needed.
- In adults: Take PRADAXA Capsules 2 times a day. If you are taking PRADAXA after hip replacement surgery, take PRADAXA 1 time a day.
- In children: Take PRADAXA Capsules 2 times a day. Take 1 dose in the morning and 1 dose in the evening about every 12 hours, at about the same time each day.
- You can take PRADAXA Capsules with or without food. Taking PRADAXA Capsules with food may help if you have an upset stomach.
- Swallow PRADAXA Capsules whole with a full glass of water. Tell your healthcare provider if you or your child are not able to swallow the capsules whole. Do not break, chew, or empty the pellets from the capsule.
- Do not run out of PRADAXA Capsules. Refill your prescription before you run out. If you plan to have surgery, or a medical or a dental procedure, tell your healthcare provider and dentist that you are taking PRADAXA. You may have to stop taking PRADAXA for a short time. See "What is the most important information I should know about PRADAXA?"
- If you miss a dose of PRADAXA Capsules, take it as soon as you remember. If your next dose is less than 6 hours away, skip the missed dose. Do not take two doses of PRADAXA Capsules at the same time.
- If you take too much PRADAXA Capsules, go to the nearest hospital emergency room or call your healthcare provider.
- Call your healthcare provider right away if you fall or injure yourself, especially if you hit your head. Your healthcare provider may need to check you.
- PRADAXA Capsules come in a bottle or in a blister package.
- Only open 1 bottle of PRADAXA Capsules at a time. Finish your opened bottle of PRADAXA Capsules before opening a new bottle.
- After opening a bottle of PRADAXA Capsules, use within 4 months. See "How should I store PRADAXA Capsules?"
- When it is time for you to take a dose of PRADAXA Capsules, only remove your prescribed dose of PRADAXA Capsules from your open bottle or blister package.
- Tightly close your bottle of PRADAXA Capsules right away after you take your dose.

What are the possible side effects of PRADAXA?
PRADAXA can cause serious side effects. See "What is the most important information I should know about PRADAXA?"

- Allergic Reactions. Some adults taking PRADAXA Capsules have developed symptoms of an allergic reaction.
  - Call your healthcare provider if you or your child gets symptoms of an allergic reaction, such as:

- hives

- rash

- itching

- Get medical help right away if you or your child gets any of the following symptoms of a serious allergic reaction with PRADAXA Capsules:

- chest pain or chest tightness
- swelling of your face or tongue

- trouble breathing or wheezing
- feeling dizzy or faint

Common side effects of PRADAXA in adults and children include:

- indigestion, upset stomach, or burning
- stomach-area (abdominal) pain or discomfort

In children, common side effects also include:

- nausea, vomiting, or diarrhea

Tell your healthcare provider if you have any side effect that bothers you or that does not go away.
These are not all of the possible side effects of PRADAXA.
Call your doctor for medical advice about side effects. You may report side effects to FDA at 1-800-FDA-1088.

How should I store PRADAXA Capsules?

- Store PRADAXA Capsules at room temperature 68°F to 77°F (20°C to 25°C).
- After opening the bottle, use PRADAXA Capsules within 4 months. Safely throw away any unused PRADAXA Capsules after 4 months.
- Keep PRADAXA Capsules in the original bottle or blister package to keep them dry (protect the capsules from moisture). Do not put PRADAXA Capsules in pill boxes or pill organizers.
- Tightly close your bottle of PRADAXA Capsules right away after you take your dose.

Keep PRADAXA Capsules and all medicines out of the reach of children.

General information about the safe and effective use of PRADAXA
Medicines are sometimes prescribed for purposes other than those listed in a Medication Guide. Do not use PRADAXA Capsules for a condition for which it was not prescribed. Do not give PRADAXA Capsules to other people, even if they have the same symptoms that you have. It may harm them.
This Medication Guide summarizes the most important information about PRADAXA. If you would like more information, talk with your healthcare provider. You can ask your pharmacist or healthcare provider for information about PRADAXA that is written for health professionals.

What are the ingredients in PRADAXA Capsules?
Active ingredient: dabigatran etexilate mesylate
Inactive ingredients: acacia, dimethicone, hydroxypropyl cellulose, hypromellose, talc, and tartaric acid. The capsule shell is composed of black edible ink, carrageenan, FD&C Blue No. 2 (150 mg and 110 mg capsules only), hypromellose, potassium chloride, and titanium dioxide.
Distributed by: Boehringer Ingelheim Pharmaceuticals, Inc. Ridgefield, CT 06877 USA
For more information about PRADAXA, including current prescribing information and Medication Guide, go to www.pradaxa.com or call Boehringer Ingelheim Pharmaceuticals, Inc. at 1-800-542-6257 or scan the code to go to www.pradaxa.com.

Copyright © 2025 Boehringer Ingelheim Pharmaceuticals, Inc.
ALL RIGHTS RESERVED
COL8774FF232025

This Medication Guide has been approved by the U.S. Food and Drug Administration.

Revised: 6/2025

PRINCIPAL DISPLAY PANEL - 110 mg Capsule Bottle Label

NDC 0597-0108-54
60 capsules

DISPENSE IN THIS UNIT OF USE CONTAINER
WITH ENCLOSED MEDICATION GUIDE

Pradaxa®
(dabigatran etexilate)
Capsules

110 mg*

Swallow capsule whole. Once opened, the product
must be used within 4 months.

Pradaxa capsules are NOT substitutable on a
mg-to-mg basis with other dabigatran etexilate
dosage forms.

PRINCIPAL DISPLAY PANEL - 75 mg Capsule Bottle Label

NDC 0597-0355-09
60 capsules

DISPENSE IN THIS UNIT OF USE CONTAINER
WITH ENCLOSED MEDICATION GUIDE

Pradaxa®
(dabigatran etexilate)
Capsules

75 mg*

Swallow capsule whole. Once opened, the product
must be used within 4 months.

Pradaxa capsules are NOT substitutable on a
mg-to-mg basis with other dabigatran etexilate
dosage forms.

PRINCIPAL DISPLAY PANEL - 150 mg Capsule Bottle Label

NDC 0597-0360-55
60 capsules

DISPENSE IN THIS UNIT OF USE CONTAINER
WITH ENCLOSED MEDICATION GUIDE

Pradaxa®
(dabigatran etexilate)
Capsules

150 mg*

Swallow capsule whole. Once opened, the product
must be used within 4 months.

Pradaxa capsules are NOT substitutable on a
mg-to-mg basis with other dabigatran etexilate
dosage forms.